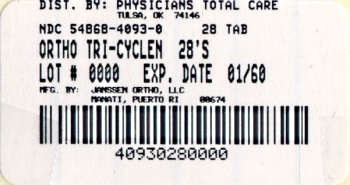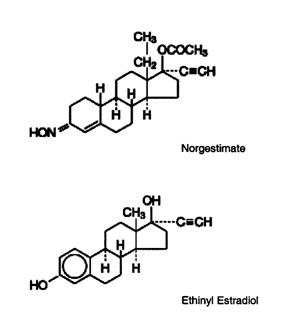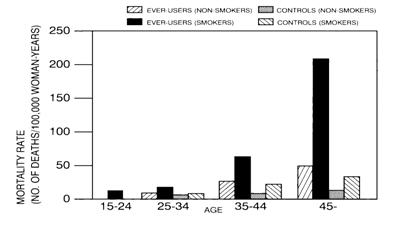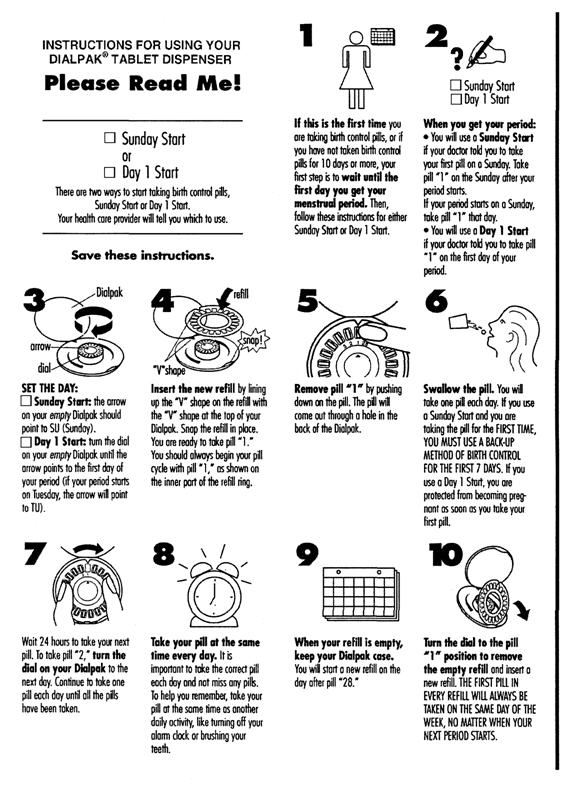 DRUG LABEL: Ortho Tri Cyclen
NDC: 54868-4093 | Form: KIT | Route: ORAL
Manufacturer: Physicians Total Care, Inc.
Category: prescription | Type: HUMAN PRESCRIPTION DRUG LABEL
Date: 20120227

ACTIVE INGREDIENTS: norgestimate 0.180 mg/1 1; ethinyl estradiol 0.035 mg/1 1; norgestimate 0.215 mg/1 1; ethinyl estradiol 0.035 mg/1 1; norgestimate 0.25 mg/1 1; ethinyl estradiol 0.035 mg/1 1
INACTIVE INGREDIENTS: Carnauba Wax; Croscarmellose Sodium; Hypromelloses; Lactose; Magnesium Stearate; Cellulose, Microcrystalline; Polyethylene Glycol; Titanium Dioxide; Water; FD&C Blue No. 2; Aluminum Oxide; Carnauba Wax; Croscarmellose Sodium; Hypromelloses; Lactose; Magnesium Stearate; Cellulose, Microcrystalline; Polyethylene Glycol; Titanium Dioxide; Water; FD&C Blue No. 2; Aluminum Oxide; Carnauba Wax; Croscarmellose Sodium; Hypromelloses; Lactose; Magnesium Stearate; Cellulose, Microcrystalline; Polyethylene Glycol; Polysorbate 80; Titanium Dioxide; Water; FD&C Blue No. 2; Aluminum Oxide; Ferric Oxide Red; Hypromelloses; Lactose; Magnesium Stearate; Polyethylene Glycol; Starch, Corn; Talc; Titanium Dioxide; Water

ORTHO TRI-CYCLEN® TABLETS
ORTHO-CYCLEN® TABLETS
(norgestimate/ethinyl estradiol)

PHYSICIANS' PACKAGE INSERT

Patients should be counseled that this product does not protect against HIV infection (AIDS) and other sexually transmitted diseases.

DESCRIPTION

Each of the following products is a combination oral contraceptive containing the progestational compound norgestimate and the estrogenic compound ethinyl estradiol.

ORTHO TRI-CYCLEN® Tablets

Each white tablet contains 0.180 mg of the progestational compound, norgestimate (18,19-Dinor-17-pregn-4-en-20-yn-3-one,17-(acetyloxy)-13-ethyl-, oxime,(17α)-(+)-) and 0.035 mg of the estrogenic compound, ethinyl estradiol (19-nor-17α-pregna,1,3,5(10)-trien-20-yne-3,17-diol). Inactive ingredients include carnauba wax, croscarmellose sodium, hypromellose, lactose, magnesium stearate, microcrystalline cellulose, polyethylene glycol, purified water and titanium dioxide.

Each light blue tablet contains 0.215 mg of the progestational compound norgestimate (18,19-Dinor-17-pregn-4-en-20-yn-3-one,17-(acetyloxy)-13-ethyl-,oxime,(17α)-(+)-) and 0.035 mg of the estrogenic compound, ethinyl estradiol (19-nor-17α-pregna,1,3,5(10)-trien-20-yne-3,17-diol). Inactive ingredients include FD & C Blue No. 2 Aluminum Lake, carnauba wax, croscarmellose sodium, hypromellose, lactose, magnesium stearate, microcrystalline cellulose, polyethylene glycol, purified water and titanium dioxide. Each blue tablet contains 0.250 mg of the progestational compound norgestimate (18,19-Dinor-17-pregn-4-en-20-yn-3-one, 17-(acetyloxy)-13-ethyl-,oxime,(17α)-(+)-) and 0.035 mg of the estrogenic compound, ethinyl estradiol (19-nor-17α-pregna,1,3,5(10)-trien-20-yne-3,17-diol). Inactive ingredients include FD & C Blue No. 2 Aluminum Lake, carnauba wax, croscarmellose sodium, hypromellose, lactose, magnesium stearate, microcrystalline cellulose, polyethylene glycol, polysorbate 80, purified water and titanium dioxide. Each dark green tablet contains only inert ingredients, as follows: FD & C Blue No. 2 Aluminum Lake, ferric oxide, hypromellose, lactose, magnesium stearate, polyethylene glycol, pregelatinized corn starch, purified water, talc and titanium dioxide.

ORTHO-CYCLEN® Tablets

Each blue tablet contains 0.250 mg of the progestational compound norgestimate (18,19-Dinor-17-pregn-4-en-20-yn-3-one,17-(acetyloxy)-13-ethyl-,oxime,(17α)-(+)-) and 0.035 mg of the estrogenic compound, ethinyl estradiol (19-nor-17α-pregna,1,3,5(10)-trien-20-yne-3,17-diol). Inactive ingredients include FD & C Blue No. 2 Aluminum Lake,carnauba wax, croscarmellose sodium, hypromellose, lactose, magnesium stearate, microcrystalline cellulose, polyethylene glycol, polysorbate 80, purified water and titanium dioxide.

Each dark green tablet contains only inert ingredients, as follows: FD & C Blue No. 2 Aluminum Lake, ferric oxide, hypromellose, lactose, magnesium stearate, polyethylene glycol, pregelatinized corn starch, purified water, talc and titanium dioxide.

CLINICAL PHARMACOLOGY

Oral Contraception

Combination oral contraceptives act by suppression of gonadotropins. Although the primary mechanism of this action is inhibition of ovulation, other alterations include changes in the cervical mucus (which increase the difficulty of sperm entry into the uterus) and the endometrium (which reduce the likelihood of implantation).

Receptor binding studies, as well as studies in animals and humans, have shown that norgestimate and 17-deacetyl norgestimate, the major serum metabolite, combine high progestational activity with minimal intrinsic androgenicity (90–93). Norgestimate, in combination with ethinyl estradiol, does not counteract the estrogen-induced increases in sex hormone binding globulin (SHBG), resulting in lower serum testosterone^90,91,94.

Acne

Acne is a skin condition with a multifactorial etiology, including androgen stimulation of sebum production. While the combination of ethinyl estradiol and norgestimate increases sex hormone binding globulin (SHBG) and decreases free testosterone, the relationship between these changes and a decrease in the severity of facial acne in otherwise healthy women with this skin condition has not been established.

PHARMACOKINETICS

Absorption

Norgestimate (NGM) and ethinyl estradiol (EE) are rapidly absorbed following oral administration. Norgestimate is rapidly and completely metabolized by firstpass (intestinal and/or hepatic) mechanisms to norelgestromin (NGMN) and norgestrel (NG), which are the major active metabolites of norgestimate.

Peak serum concentrations of NGMN and EE are generally reached by 2 hours after administration of ORTHO-CYCLEN® or ORTHO TRI-CYCLEN®. Accumulation following multiple dosing of the 250 µg NGM / 35 µg dose is approximately 2-fold for NGMN and EE compared with single dose administration. The pharmacokinetics of NGMN is dose proportional following NGM doses of 180 µg to 250 µg. Steady-state concentration of EE is achieved by Day 7 of each dosing cycle. Steady-state concentrations of NGMN and NG are achieved by Day 21. Non-linear accumulation (approximately 8 fold) of norgestrel is observed as a result of high affinity binding to SHBG (sex hormone-binding globulin), which limits its biological activity. Table 1. Summary of norelgestromin, norgestrel and ethinyl estradiol pharmacokinetic parameters.

Mean (SD) Pharmacokinetic Parameters of ORTHO TRI-CYCLEN During a Three Cycle Study
Analyte | Cycle | Day | Cmax | tmax (h) | AUC0–24h | t1/2 (h)
NGMN | 3 | 7 | 1.80 (0.46) | 1.42 (0.73) | 15.0 (3.88) | NC
 |  | 14 | 2.12 (0.56) | 1.21 (0.26) | 16.1 (4.97) | NC
 |  | 21 | 2.66 (0.47) | 1.29 (0.26) | 21.4 (3.46) | 22.3 (6.54)
NG | 3 | 7 | 1.94 (0.82) | 3.15 (4.05) | 34.8 (16.5) | NC
 |  | 14 | 3.00 (1.04) | 2.21 (2.03) | 55.2 (23.5) | NC
 |  | 21 | 3.66 (1.15) | 2.58 (2.97) | 69.3 (23.8) | 40.2 (15.4)
EE | 3 | 7 | 124 (39.5) | 1.27 (0.26) | 1130 (420) | NC
 |  | 14 | 128 (38.4) | 1.32 (0.25) | 1130 (324) | NC
 |  | 21 | 126 (34.7) | 1.31 (0.56) | 1090 (359) | 15.9 (4.39)
Mean (SD) Pharmacokinetic Parameters of ORTHO-CYCLEN During a Three Cycle Study
Analyte | Cycle | Day | Cmax | tmax (h) | AUC0–24h | t1/2 (h)
NGMN | 1 | 1 | 1.78 (0.397) | 1.19 (0.250) | 9.90 (3.25) | 18.4 (5.91)
 | 3 | 21 | 2.19 (0.655) | 1.43 (0.680) | 18.1 (5.53) | 24.9 (9.04)
NG | 1 | 1 | 0.649 (0.49) | 1.42 (0.69) | 6.22 (2.46) | 37.8 (14.0)
 | 3 | 21 | 2.65 (1.11) | 1.67 (1.32) | 48.2 (20.5) | 45.0 (20.4)
EE | 1 | 1 | 92.2 (24.5) | 1.2 (0.26) | 629 (138) | 10.1 (1.90)
 | 3 | 21 | 147 (41.5) | 1.13 (0.23) | 1210 (294) | 15.0 (2.36)
Cmax = peak serum concentration, tmax = time to reach peak serum concentration, AUC0–24h = area under serum concentration vs time curve from 0 to 24 hours, t1/2 = elimination half-life, NC = not calculated.
NGMN and NG: Cmax = ng/mL, AUC0–24h=h∙ng/mL
EE: Cmax=pg/mL, AUC0–24h=h∙pg/mL

The effect of food on the pharmacokinetics of ORTHO-CYCLEN or ORTHO TRI-CYCLEN has not been studied.

Distribution

Norelgestromin and norgestrel are highly bound (>97%) to serum proteins. Norelgestromin is bound to albumin and not to SHBG, while norgestrel is bound primarily to SHBG. Ethinyl estradiol is extensively bound (> 97%) to serum albumin and induces an increase in the serum concentrations of SHBG.

Metabolism

Norgestimate is extensively metabolized by first-pass mechanisms in the gastrointestinal tract and/or liver. Norgestimate's primary active metabolite is norelgestromin. Subsequent hepatic metabolism of norelgestromin occurs and metabolites include norgestrel, which is also active and various hydroxylated and conjugated metabolites. Ethinyl estradiol is also metabolized to various hydroxylated products and their glucuronide and sulfate conjugates.

Excretion

The metabolites of norelgestromin and ethinyl estradiol are eliminated by renal and fecal pathways. Following administration of ^14C-norgestimate, 47% (45–49%) and 37% (16–49%) of the administered radioactivity was eliminated in the urine and feces, respectively. Unchanged norgestimate was not detected in the urine. In addition to 17-deacetyl norgestimate, a number of metabolites of norgestimate have been identified in human urine following administration of radiolabeled norgestimate. These include 18, 19-Dinor-17-pregn-4-en-20-yn-3-one,17-hydroxy-13-ethyl,(17α)-(-);18,19-Dinor-5β -17-pregnan-20-yn,3α ,17β-dihydroxy-13-ethyl,(17α), various hydroxylated metabolites and conjugates of these metabolites.

Special Populations

The effects of body weight, body surface area or age on the pharmacokinetics of ORTHO-CYCLEN® or ORTHO TRI-CYCLEN® have not been studied.

Hepatic Impairment

The effects of hepatic impairment on the pharmacokinetics of ORTHO-CYCLEN® or ORTHO TRI-CYCLEN® have not been studied. However, steroid hormones may be poorly metabolized in women with impaired liver function (see PRECAUTIONS).

Renal Impairment

The effects of renal impairment on the pharmacokinetics of ORTHO-CYCLEN® or ORTHO TRI-CYCLEN® have not been studied.

Drug-Drug Interactions

No formal drug-drug interaction studies were conducted with ORTHO-CYCLEN® or ORTHO TRI-CYCLEN®. Interactions between contraceptive steroids and other drugs have been reported in the literature (see PRECAUTIONS).

Although norelgestromin and its metabolites inhibit a variety of P450 enzymes in human liver microsomes, under the recommended dosing regimen, the in vivo concentrations of norelgestromin and its metabolites, even at the peak serum levels, are relatively low compared to the inhibitory constant (Ki).

INDICATIONS AND USAGE

ORTHO-CYCLEN® and ORTHO TRI-CYCLEN® Tablets are indicated for the prevention of pregnancy in women who elect to use oral contraceptives as a method of contraception.

ORTHO TRI-CYCLEN is indicated for the treatment of moderate acne vulgaris in females at least 15 years of age, who have no known contraindications to oral contraceptive therapy and have achieved menarche. ORTHO TRI-CYCLEN should be used for the treatment of acne only if the patient desires an oral contraceptive for birth control.

Oral contraceptives are highly effective for pregnancy prevention. Table II lists the typical accidental pregnancy rates for users of combination oral contraceptives and other methods of contraception. The efficacy of these contraceptive methods, except sterilization, the IUD, and the Norplant System, depends upon the reliability with which they are used. Correct and consistent use of methods can result in lower failure rates.

Table II: Percentage of Women Experiencing an Unintended Pregnancy During the First Year of Typical Use and the First Year of Perfect Use of Contraception and the Percentage Continuing Use at the End of the First Year. United States.
 | % of Women Experiencing an Unintended Pregnancy within the First Year of Use |  | % of Women Continuing Use at One Year [Among couples attempting to avoid pregnancy, the percentage who continue to use a method for one year.]
Method | Typical Use [Among typical couples who initiate use of a method (not necessarily for the first time), the percentage who experience an accidental pregnancy during the first year if they do not stop use for any other reason.] | Perfect Use [Among couples who initiate use of a method (not necessarily for the first time) and who use it perfectly (both consistently and correctly), the percentage who experience an accidental pregnancy during the first year if they do not stop use for any other reason.] | % of Women Continuing Use at One Year [Among couples attempting to avoid pregnancy, the percentage who continue to use a method for one year.]
(1) | (2) | (3) | (4)
Chance [The percents becoming pregnant in columns (2) and (3) are based on data from populations where contraception is not used and from women who cease using contraception in order to become pregnant. Among such populations, about 89% become pregnant within one year. This estimate was lowered slightly (to 85%) to represent the percent who would become pregnant within one year among women now relying on reversible methods of contraception if they abandoned contraception altogether.] | 85 | 85
Spermicides [Foams, creams, gels, vaginal suppositories, and vaginal film.] | 26 | 6 | 40
Periodic abstinence | 25 |  | 63
Calendar |  | 9
Ovulation Method |  | 3
Sympto-Thermal [Cervical mucus (ovulation) method supplemented by calendar in the pre-ovulatory and basal body temperature in the post-ovulatory phases.] |  | 2
Post-Ovulation |  | 1
Cap [With spermicidal cream or jelly.]
Parous Women | 40 | 26 | 42
Nulliparous Women | 20 | 9 | 56
Sponge
Parous Women | 40 | 20 | 42
Nulliparous Women | 20 | 9 | 56
Diaphragm | 20 | 6 | 56
Withdrawal | 19 | 4
Condom [Without spermicides.]
Female (Reality) | 21 | 5 | 56
Male | 14 | 3 | 61
Pill | 5 |  | 71
Progestin Only |  | 0.5
Combined |  | 0.1
IUD
Progesterone T | 2.0 | 1.5 | 81
Copper T380A | 0.8 | 0.6 | 78
LNg 20 | 0.1 | 0.1 | 81
Depo-Provera | 0.3 | 0.3 | 70
Norplant and Norplant-2 | 0.05 | 0.05 | 88
Female Sterilization | 0.5 | 0.5 | 100
Male Sterilization | 0.15 | 0.10 | 100
Hatcher et al, 1998, Ref. # 1.
Emergency Contraceptive Pills: Treatment initiated within 72 hours after unprotected intercourse reduces the risk of pregnancy by at least 75%. [The treatment schedule is one dose within 72 hours after unprotected intercourse, and a second dose 12 hours after the first dose. The Food and Drug Administration has declared the following brands of oral contraceptives to be safe and effective for emergency contraception: Ovral® (1 dose is 2 white pills), Alesse® (1 dose is 5 pink pills), Nordette® or Levlen® (1 dose is 2 light-orange pills), Lo/Ovral® (1 dose is 4 white pills), Triphasil® or Tri-Levlen® (1 dose is 4 yellow pills).]
Lactational Amenorrhea Method: LAM is highly effective, temporary method of contraception. [However, to maintain effective protection against pregnancy, another method of contraception must be used as soon as menstruation resumes, the frequency or duration of breastfeeds is reduced, bottle feeds are introduced, or the baby reaches six months of age.]
Source: Trussell J, Contraceptive efficacy. In Hatcher RA, Trussell J, Stewart F, Cates W, Stewart GK, Kowal D, Guest F, Contraceptive Technology: Seventeenth Revised Edition. New York NY: Irvington Publishers, 1998.

ORTHO-CYCLEN and ORTHO TRI-CYCLEN have not been studied for and are not indicated for use in emergency contraception.

In clinical trials with ORTHO-CYCLEN, 1,651 subjects completed 24,272 cycles and the overall use-efficacy (typical user efficacy) pregnancy rate was approximately 1 pregnancy per 100 women-years. This rate includes patients who did not take the drug correctly.

In four clinical trials with ORTHO TRI-CYCLEN, a total of 4,756 subjects completed 45,244 cycles, and the use-efficacy pregnancy rate was approximately 1 pregnancy per 100 women-years.

ORTHO TRI-CYCLEN was evaluated for the treatment of acne vulgaris in two randomized, double-blind, placebo-controlled, multicenter, Phase 3, six (28 day) cycle studies. 221 patients received ORTHO TRI-CYCLEN and 234 patients received placebo. Mean age at enrollment for both groups was 28 years. At the end of 6 months, the mean total lesion count changes from 55 to 31 (42% reduction) in patients treated with ORTHO TRI-CYCLEN and from 54 to 38 (27% reduction) in patients similarly treated with placebo. Table III summarizes the changes in lesion count for each type of lesion in the ITT population. Based on the investigator's global assessment conducted at the final visit, patients treated with ORTHO TRI-CYCLEN showed a statistically significant improvement in total lesions compared to those treated with placebo.

Table III: Acne Vulgaris Indication. Combined Results: Two Multicenter, Placebo-Controlled Trials. Observed Means at Six Months (LOCF) [LOCF: Last Observation Carried Forward] and at Baseline. Intent-to-Treat Population.
 | ORTHO TRI-CYCLEN (N=221) |  | Placebo (N=234) |  | Difference in Counts between ORTHO TRI-CYCLEN and Placebo at 6 Months
# of Lesions | Counts | % Reduction | Counts | % Reduction
INFLAMMATORY LESIONS
Baseline Mean | 19 |  | 19
Sixth Month Mean | 10 | 48% | 13 | 30% | 3 (95 % CI: -1.2, 5.1)
NON-INFLAMMATORY LESIONS
Baseline Mean | 36 |  | 35
Sixth Month Mean | 22 | 34% | 25 | 21% | 3 (95% CI: -0.2, 7.8)
TOTAL LESIONS
Baseline Mean | 55 |  | 54
Sixth Month Mean | 31 | 42% | 38 | 27% | 7 (95% CI: 2.0, 11.9)

CONTRAINDICATIONS

Oral contraceptives should not be used in women who currently have the following conditions:

- Thrombophlebitis or thromboembolic disorders
- A past history of deep vein thrombophlebitis or thromboembolic disorders
- Cerebral vascular or coronary artery disease (current or past history)
- Valvular heart disease with complications
- Severe hypertension
- Diabetes with vascular involvement
- Headaches with focal neurological symptoms
- Major surgery with prolonged immobilization
- Known or suspected carcinoma of the breast or personal history of breast cancer
- Carcinoma of the endometrium or other known or suspected estrogen-dependent neoplasia
- Undiagnosed abnormal genital bleeding
- Cholestatic jaundice of pregnancy or jaundice with prior pill use
- Acute or chronic hepatocellular disease with abnormal liver function
- Hepatic adenomas or carcinomas
- Known or suspected pregnancy
- Hypersensitivity to any component of this product

WARNINGS

BOXED WARNING

Cigarette smoking increases the risk of serious cardiovascular side effects from oral contraceptive use. This risk increases with age and with heavy smoking (15 or more cigarettes per day) and is quite marked in women over 35 years of age. Women who use oral contraceptives should be strongly advised not to smoke.

The use of oral contraceptives is associated with increased risks of several serious conditions including myocardial infarction, thromboembolism, stroke, hepatic neoplasia, and gallbladder disease, although the risk of serious morbidity or mortality is very small in healthy women without underlying risk factors. The risk of morbidity and mortality increases significantly in the presence of other underlying risk factors such as hypertension, hyperlipidemias, obesity and diabetes.

Practitioners prescribing oral contraceptives should be familiar with the following information relating to these risks.

The information contained in this package insert is principally based on studies carried out in patients who used oral contraceptives with higher formulations of estrogens and progestogens than those in common use today. The effect of long-term use of the oral contraceptives with lower formulations of both estrogens and progestogens remains to be determined.

Throughout this labeling, epidemiological studies reported are of two types: retrospective or case control studies and prospective or cohort studies. Case control studies provide a measure of the relative risk of a disease, namely, a ratio of the incidence of a disease among oral contraceptive users to that among nonusers. The relative risk does not provide information on the actual clinical occurrence of a disease. Cohort studies provide a measure of attributable risk, which is the difference in the incidence of disease between oral contraceptive users and nonusers. The attributable risk does provide information about the actual occurrence of a disease in the population (adapted from refs. 2 and 3 with the author's permission). For further information, the reader is referred to a text on epidemiological methods.

1. Thromboembolic Disorders and Other Vascular Problems

a. Myocardial Infarction

An increased risk of myocardial infarction has been attributed to oral contraceptive use. This risk is primarily in smokers or women with other underlying risk factors for coronary artery disease such as hypertension, hypercholesterolemia, morbid obesity, and diabetes. The relative risk of heart attack for current oral contraceptive users has been estimated to be two to six ^4–10 . The risk is very low under the age of 30.

Smoking in combination with oral contraceptive use has been shown to contribute substantially to the incidence of myocardial infarctions in women in their mid-thirties or older with smoking accounting for the majority of excess cases^11. Mortality rates associated with circulatory disease have been shown to increase substantially in smokers, especially in those 35 years of age and older and in nonsmokers over the age of 40 among women who use oral contraceptives.

Figure 1. Circulatory Disease Mortality Rates Per 100,000 Women-Years By Age, Smoking Status and Oral Contraceptive Use

(Adapted from P.M. Layde and V. Beral, ref. #12.)

Oral contraceptives may compound the effects of well-known risk factors, such as hypertension, diabetes, hyperlipidemias, age and obesity^13. In particular, some progestogens are known to decrease HDL cholesterol and cause glucose intolerance, while estrogens may create a state of hyperinsulinism^14–18. Oral contraceptives have been shown to increase blood pressure among users (see Section 9 in WARNINGS). Similar effects on risk factors have been associated with an increased risk of heart disease. Oral contraceptives must be used with caution in women with cardiovascular disease risk factors.

Norgestimate has minimal androgenic activity (see CLINICAL PHARMACOLOGY), and there is some evidence that the risk of myocardial infarction associated with oral contraceptives is lower when the progestogen has minimal androgenic activity than when the activity is greater^97.

b. Thromboembolism

An increased risk of thromboembolic and thrombotic disease associated with the use of oral contraceptives is well established. Case control studies have found the relative risk of users compared to nonusers to be 3 for the first episode of superficial venous thrombosis, 4 to 11 for deep vein thrombosis or pulmonary embolism, and 1.5 to 6 for women with predisposing conditions for venous thromboembolic disease^2,3,19–24. Cohort studies have shown the relative risk to be somewhat lower, about 3 for new cases and about 4.5 for new cases requiring hospitalization^25. The risk of thromboembolic disease associated with oral contraceptives is not related to length of use and disappears after pill use is stopped^2.

A two- to four-fold increase in relative risk of post-operative thromboembolic complications has been reported with the use of oral contraceptives^9. The relative risk of venous thrombosis in women who have predisposing conditions is twice that of women without such medical conditions^26. If feasible, oral contraceptives should be discontinued at least four weeks prior to and for two weeks after elective surgery of a type associated with an increase in risk of thromboembolism and during and following prolonged immobilization. Since the immediate postpartum period is also associated with an increased risk of thromboembolism, oral contraceptives should be started no earlier than four weeks after delivery in women who elect not to breast feed.

c. Cerebrovascular Diseases

Oral contraceptives have been shown to increase both the relative and attributable risks of cerebrovascular events (thrombotic and hemorrhagic strokes), although, in general, the risk is greatest among older (>35 years), hypertensive women who also smoke. Hypertension was found to be a risk factor for both users and nonusers, for both types of strokes, and smoking interacted to increase the risk of stroke^27–29.

In a large study, the relative risk of thrombotic strokes has been shown to range from 3 for normotensive users to 14 for users with severe hypertension^30. The relative risk of hemorrhagic stroke is reported to be 1.2 for non-smokers who used oral contraceptives, 2.6 for smokers who did not use oral contraceptives, 7.6 for smokers who used oral contraceptives, 1.8 for normotensive users and 25.7 for users with severe hypertension^30. The attributable risk is also greater in older women^3.

d. Dose-Related Risk of Vascular Disease From Oral Contraceptives

A positive association has been observed between the amount of estrogen and progestogen in oral contraceptives and the risk of vascular disease^31–33. A decline in serum high density lipoproteins (HDL) has been reported with many progestational agents^14–16. A decline in serum high density lipoproteins has been associated with an increased incidence of ischemic heart disease. Because estrogens increase HDL cholesterol, the net effect of an oral contraceptive depends on a balance achieved between doses of estrogen and progestogen and the activity of the progestogen used in the contraceptives. The activity and amount of both hormones should be considered in the choice of an oral contraceptive.

Minimizing exposure to estrogen and progestogen is in keeping with good principles of therapeutics. For any particular estrogen/progestogen combination, the dosage regimen prescribed should be one which contains the least amount of estrogen and progestogen that is compatible with a low failure rate and the needs of the individual patient. New acceptors of oral contraceptive agents should be started on preparations containing the lowest estrogen content which is judged appropriate for the individual patient.

e. Persistence of Risk of Vascular Disease

There are two studies which have shown persistence of risk of vascular disease for ever-users of oral contraceptives. In a study in the United States, the risk of developing myocardial infarction after discontinuing oral contraceptives persists for at least 9 years for women 40–49 years who had used oral contraceptives for five or more years, but this increased risk was not demonstrated in other age groups^8. In another study in Great Britain, the risk of developing cerebrovascular disease persisted for at least 6 years after discontinuation of oral contraceptives, although excess risk was very small^34. However, both studies were performed with oral contraceptive formulations containing 50 micrograms or higher of estrogens.

2. Estimates of Mortality From Contraceptive Use

One study gathered data from a variety of sources which have estimated the mortality rate associated with different methods of contraception at different ages (Table IV). These estimates include the combined risk of death associated with contraceptive methods plus the risk attributable to pregnancy in the event of method failure. Each method of contraception has its specific benefits and risks. The study concluded that with the exception of oral contraceptive users 35 and older who smoke, and 40 and older who do not smoke, mortality associated with all methods of birth control is low and below that associated with childbirth. The observation of an increase in risk of mortality with age for oral contraceptive users is based on data gathered in the 1970's^35. Current clinical recommendation involves the use of lower estrogen dose formulations and a careful consideration of risk factors. In 1989, the Fertility and Maternal Health Drugs Advisory Committee was asked to review the use of oral contraceptives in women 40 years of age and over. The Committee concluded that although cardiovascular disease risks may be increased with oral contraceptive use after age 40 in healthy non-smoking women (even with the newer low-dose formulations), there are also greater potential health risks associated with pregnancy in older women and with the alternative surgical and medical procedures which may be necessary if such women do not have access to effective and acceptable means of contraception. The Committee recommended that the benefits of low-dose oral contraceptive use by healthy non-smoking women over 40 may outweigh the possible risks.

Of course, older women, as all women, who take oral contraceptives, should take an oral contraceptive which contains the least amount of estrogen and progestogen that is compatible with a low failure rate and individual patient needs.

Table IV: Annual Number of Birth-Related or Method-Related Deaths Associated With Control of Fertility Per 100,000 Non-Sterile Women, by Fertility Control Method According to Age
Method of control and outcome | 15–19 | 20–24 | 25–29 | 30–34 | 35–39 | 40–44
No fertility control methods [Deaths are birth-related] | 7.0 | 7.4 | 9.1 | 14.8 | 25.7 | 28.2
Oral contraceptives non-smoker [Deaths are method-related] | 0.3 | 0.5 | 0.9 | 1.9 | 13.8 | 31.6
Oral contraceptives, smoker | 2.2 | 3.4 | 6.6 | 13.5 | 51.1 | 117.2
IUD | 0.8 | 0.8 | 1.0 | 1.0 | 1.4 | 1.4
Condom | 1.1 | 1.6 | 0.7 | 0.2 | 0.3 | 0.4
Diaphragm/spermicide | 1.9 | 1.2 | 1.2 | 1.3 | 2.2 | 2.8
Periodic abstinence | 2.5 | 1.6 | 1.6 | 1.7 | 2.9 | 3.6
Adapted from H.W. Ory, ref. #35.

3. Carcinoma of the Reproductive Organs and Breasts

Numerous epidemiological studies have been performed on the incidence of breast, endometrial, ovarian, and cervical cancer in women using oral contraceptives. The risk of having breast cancer diagnosed may be slightly increased among current and recent users of combination oral contraceptives (COCs). However, this excess risk appears to decrease over time after COC discontinuation and by 10 years after cessation the increased risk disappears. Some studies report an increased risk with duration of use while other studies do not and no consistent relationships have been found with dose or type of steroid. Some studies have found a small increase in risk for women who first use COCs before age 20. Most studies show a similar pattern of risk with COC use regardless of a woman's reproductive history or her family breast cancer history.

Breast cancers diagnosed in current or previous oral contraceptive users tend to be less clinically advanced than nonusers. Women who currently have or have had breast cancer should not use oral contraceptives because breast cancer is usually a hormonally-sensitive tumor.

Some studies suggest that oral contraceptive use has been associated with an increase in the risk of cervical intraepithelial neoplasia in some populations of women^45–48. However, there continues to be controversy about the extent to which such findings may be due to differences in sexual behavior and other factors. In spite of many studies of the relationship between oral contraceptive use and breast and cervical cancers, a cause-and-effect relationship has not been established.

4. Hepatic Neoplasia

Benign hepatic adenomas are associated with oral contraceptive use, although the incidence of benign tumors is rare in the United States. Indirect calculations have estimated the attributable risk to be in the range of 3.3 cases/100,000 for users, a risk that increases after four or more years of use especially with oral contraceptives of higher dose^49. Rupture of benign, hepatic adenomas may cause death through intra-abdominal hemorrhage^50,51.

Studies from Britain have shown an increased risk of developing hepatocellular carcinoma in long-term (>8 years) oral contraceptive users. However, these cancers are extremely rare in the U.S. and the attributable risk (the excess incidence) of liver cancers in oral contraceptive users approaches less than one per million users.

5. Ocular Lesions

There have been clinical case reports of retinal thrombosis associated with the use of oral contraceptives. Oral contraceptives should be discontinued if there is unexplained partial or complete loss of vision; onset of proptosis or diplopia; papilledema; or retinal vascular lesions. Appropriate diagnostic and therapeutic measures should be undertaken immediately.

6. Oral Contraceptive Use Before or During Early Pregnancy

Extensive epidemiological studies have revealed no increased risk of birth defects in women who have used oral contraceptives prior to pregnancy^56,57 . The majority of recent studies also do not indicate a teratogenic effect, particularly in so far as cardiac anomalies and limb reduction defects are concerned^55,56,58,59 when taken inadvertently during early pregnancy.

The administration of oral contraceptives to induce withdrawal bleeding should not be used as a test for pregnancy. Oral contraceptives should not be used during pregnancy to treat threatened or habitual abortion.

It is recommended that for any patient who has missed two consecutive periods, pregnancy should be ruled out. If the patient has not adhered to the prescribed schedule, the possibility of pregnancy should be considered at the time of the first missed period. Oral contraceptive use should be discontinued if pregnancy is confirmed.

7. Gallbladder Disease

Earlier studies have reported an increased lifetime relative risk of gallbladder surgery in users of oral contraceptives and estrogens^60,61. More recent studies, however, have shown that the relative risk of developing gallbladder disease among oral contraceptive users may be minimal^62–64. The recent findings of minimal risk may be related to the use of oral contraceptive formulations containing lower hormonal doses of estrogens and progestogens.

8. Carbohydrate and Lipid Metabolic Effects

Oral contraceptives have been shown to cause a decrease in glucose tolerance in a significant percentage of users^17. This effect has been shown to be directly related to estrogen dose^65. Progestogens increase insulin secretion and create insulin resistance, this effect varying with different progestational agents^17,66. However, in the non-diabetic woman, oral contraceptives appear to have no effect on fasting blood glucose^67. Because of these demonstrated effects, prediabetic and diabetic women in particular should be carefully monitored while taking oral contraceptives.

A small proportion of women will have persistent hypertriglyceridemia while on the pill. As discussed earlier (see WARNINGS 1a and 1d), changes in serum triglycerides and lipoprotein levels have been reported in oral contraceptive users.

In clinical studies with ORTHO-CYCLEN® there were no clinically significant changes in fasting blood glucose levels. No statistically significant changes in mean fasting blood glucose levels were observed over 24 cycles of use. Glucose tolerance tests showed minimal, clinically insignificant changes from baseline to cycles 3, 12, and 24.

In clinical studies with ORTHO TRI-CYCLEN® there were no clinically significant changes in fasting blood glucose levels. Minimal statistically significant changes were noted in glucose levels over 24 cycles of use. Glucose tolerance tests showed no clinically significant changes from baseline to cycles 3, 12, and 24.

9. Elevated Blood Pressure

Women with significant hypertension should not be started on hormonal contraception^98. An increase in blood pressure has been reported in women taking oral contraceptives^68 and this increase is more likely in older oral contraceptive users^69 and with extended duration of use^61. Data from the Royal College of General Practitioners^12 and subsequent randomized trials have shown that the incidence of hypertension increases with increasing progestational activity.

Women with a history of hypertension or hypertension-related diseases, or renal disease^70 should be encouraged to use another method of contraception. If women elect to use oral contraceptives, they should be monitored closely and if significant elevation of blood pressure occurs, oral contraceptives should be discontinued. For most women, elevated blood pressure will return to normal after stopping oral contraceptives, and there is no difference in the occurrence of hypertension between former and never users^68–71. It should be noted that in two separate large clinical trials (N=633 and N=911), no statistically significant changes in mean blood pressure were observed with ORTHO-CYCLEN®.

10. Headache

The onset or exacerbation of migraine or development of headache with a new pattern which is recurrent, persistent or severe requires discontinuation of oral contraceptives and evaluation of the cause.

11. Bleeding Irregularities

Breakthrough bleeding and spotting are sometimes encountered in patients on oral contraceptives, especially during the first three months of use. Non-hormonal causes should be considered and adequate diagnostic measures taken to rule out malignancy or pregnancy in the event of breakthrough bleeding, as in the case of any abnormal vaginal bleeding. If pathology has been excluded, time or a change to another formulation may solve the problem. In the event of amenorrhea, pregnancy should be ruled out.

Some women may encounter post-pill amenorrhea or oligomenorrhea, especially when such a condition was preexistent.

12. Ectopic Pregnancy

Ectopic as well as intrauterine pregnancy may occur in contraceptive failures.

PRECAUTIONS

1. General

Patients should be counseled that this product does not protect against HIV infection (AIDS) and other sexually transmitted diseases.

2. Physical Examination and Follow Up

It is good medical practice for all women to have annual history and physical examinations, including women using oral contraceptives. The physical examination, however, may be deferred until after initiation of oral contraceptives if requested by the woman and judged appropriate by the clinician. The physical examination should include special reference to blood pressure, breasts, abdomen and pelvic organs, including cervical cytology, and relevant laboratory tests. In case of undiagnosed, persistent or recurrent abnormal vaginal bleeding, appropriate measures should be conducted to rule out malignancy. Women with a strong family history of breast cancer or who have breast nodules should be monitored with particular care.

3. Lipid Disorders

Women who are being treated for hyperlipidemias should be followed closely if they elect to use oral contraceptives. Some progestogens may elevate LDL levels and may render the control of hyperlipidemias more difficult.

4. Liver Function

If jaundice develops in any woman receiving such drugs, the medication should be discontinued. Steroid hormones may be poorly metabolized in patients with impaired liver function.

5. Fluid Retention

Oral contraceptives may cause some degree of fluid retention. They should be prescribed with caution, and only with careful monitoring, in patients with conditions which might be aggravated by fluid retention.

6. Emotional Disorders

Women with a history of depression should be carefully observed and the drug discontinued if depression recurs to a serious degree.

7. Contact Lenses

Contact lens wearers who develop visual changes or changes in lens tolerance should be assessed by an ophthalmologist.

8. Drug Interactions

Changes in contraceptive effectiveness associated with co-administration of other products

Contraceptive effectiveness may be reduced when hormonal contraceptives are co-administered with antibiotics, anticonvulsants, and other drugs that increase the metabolism of contraceptive steroids. This could result in unintended pregnancy or breakthrough bleeding. Examples include rifampin, barbiturates, phenylbutazone, phenytoin, carbamazepine, felbamate, oxcarbazepine, topiramate, griseofulvin and bosentan.

Several of the anti-HIV protease inhibitors have been studied with co-administration of oral combination hormonal contraceptives; significant changes (increase and decrease) in the plasma levels of the estrogen and progestin have been noted in some cases. The safety and efficacy of oral contraceptive products may be affected with co-administration of anti-HIV protease inhibitors. Healthcare professionals should refer to the label of the individual anti-HIV protease inhibitors for further drug-drug interaction information.

Herbal products containing St. John's Wort (hypericum perforatum) may induce hepatic enzymes (cytochrome P450) and p-glycoprotein transporter and may reduce the effectiveness of contraceptive steroids. This may also result in breakthrough bleeding.

Concurrent use of bosentan and ethinyl estradiol containing products may result in decreased concentrations of these contraceptive hormones thereby increasing the risk of unintended pregnancy and unscheduled bleeding.

Increase in plasma levels associated with co-administered drugs

Co-administration of atorvastatin and certain oral contraceptives containing ethinyl estradiol increase AUC values for ethinyl estradiol by approximately 20%. Ascorbic acid and acetaminophen may increase plasma ethinyl estradiol levels, possibly by inhibition of conjugation. CYP 3A4 inhibitors such as itraconazole or ketoconazole may increase plasma hormone levels.

Changes in plasma levels of co-administered drugs

Combination hormonal contraceptives containing some synthetic estrogens (e.g., ethinyl estradiol) may inhibit the metabolism of other compounds. Increased plasma concentrations of cyclosporine, prednisolone, and theophylline have been reported with concomitant administration of oral contraceptives. Decreased plasma concentrations of acetaminophen and increased clearance of temazepam, salicylic acid, morphine and clofibric acid, due to induction of conjugation, have been noted when these drugs were administered with oral contraceptives.

Combined hormonal contraceptives have been shown to significantly decrease plasma concentrations of lamotrigine when co-administered due to induction of lamotrigine glucuronidation. This may reduce seizure control; therefore, dosage adjustments of lamotrigine may be necessary.^101

Healthcare professionals are advised to also refer to prescribing information of co-administered drugs for recommendations regarding management of concomitant therapy.

9. Interactions with Laboratory Tests

Certain endocrine and liver function tests and blood components may be affected by oral contraceptives:

1. Increased prothrombin and factors VII, VIII, IX, and X; decreased antithrombin 3; increased norepinephrine-induced platelet aggregability.
2. Increased thyroid binding globulin (TBG) leading to increased circulating total thyroid hormone, as measured by protein-bound iodine (PBI), T4 by column or by radioimmunoassay. Free T3 resin uptake is decreased, reflecting the elevated TBG, free T4 concentration is unaltered.
3. Other binding proteins may be elevated in serum.
4. Sex hormone binding globulins are increased and result in elevated levels of total circulating sex steroids; however, free or biologically active levels either decrease or remain unchanged.
5. Triglycerides may be increased and levels of various other lipids and lipoproteins may be affected.
6. Glucose tolerance may be decreased.
7. Serum folate levels may be depressed by oral contraceptive therapy. This may be of clinical significance if a woman becomes pregnant shortly after discontinuing oral contraceptives.

10. Carcinogenesis

See WARNINGS Section.

11. Pregnancy

Pregnancy Category X

See CONTRAINDICATIONS and WARNINGS Sections.

12. Nursing Mothers

Small amounts of oral contraceptive steroids have been identified in the milk of nursing mothers and a few adverse effects on the child have been reported, including jaundice and breast enlargement. In addition, combination oral contraceptives given in the postpartum period may interfere with lactation by decreasing the quantity and quality of breast milk. If possible, the nursing mother should be advised not to use combination oral contraceptives but to use other forms of contraception until she has completely weaned her child.

13. Pediatric Use

Safety and efficacy of ORTHO TRI-CYCLEN® Tablets and ORTHO-CYCLEN® Tablets have been established in women of reproductive age. Safety and efficacy are expected to be the same for postpubertal adolescents under the age of 16 and for users 16 years and older. There was no significant difference between ORTHO TRI-CYCLEN Tablets and placebo in mean change in total lumbar spine (L1–L4) and total hip bone mineral density between baseline and Cycle 13 in 123 adolescent females with anorexia nervosa in a double-blind, placebo-controlled, multicenter, one-year treatment duration clinical trial for the Intent To Treat (ITT) population. Use of this product before menarche is not indicated.

14. Geriatric Use

This product has not been studied in women over 65 years of age and is not indicated in this population.

INFORMATION FOR THE PATIENT

See Patient Labeling printed below.

ADVERSE REACTIONS

An increased risk of the following serious adverse reactions has been associated with the use of oral contraceptives (see WARNINGS Section).

- Thrombophlebitis and venous thrombosis with or without embolism
- Arterial thromboembolism
- Pulmonary embolism
- Myocardial infarction
- Cerebral hemorrhage
- Cerebral thrombosis
- Hypertension
- Gallbladder disease
- Hepatic adenomas or benign liver tumors

There is evidence of an association between the following conditions and the use of oral contraceptives:

- Mesenteric thrombosis
- Retinal thrombosis

The following adverse reactions have been reported in patients receiving oral contraceptives and are believed to be drug-related:

- Nausea
- Vomiting
- Gastrointestinal symptoms (such as abdominal cramps and bloating)
- Breakthrough bleeding
- Spotting
- Change in menstrual flow
- Amenorrhea
- Temporary infertility after discontinuation of treatment
- Edema
- Melasma which may persist
- Breast changes: tenderness, enlargement, secretion
- Change in weight (increase or decrease)
- Change in cervical erosion and secretion
- Diminution in lactation when given immediately postpartum
- Cholestatic jaundice
- Migraine
- Allergic reaction, including rash, urticaria, angioedema
- Mental depression
- Reduced tolerance to carbohydrates
- Vaginal candidiasis
- Change in corneal curvature (steepening)
- Intolerance to contact lenses

The following adverse reactions have been reported in users of oral contraceptives and a causal association has been neither confirmed nor refuted:

- Pre-menstrual syndrome
- Cataracts
- Changes in appetite
- Cystitis-like syndrome
- Headache
- Nervousness
- Dizziness
- Hirsutism
- Loss of scalp hair
- Erythema multiforme
- Erythema nodosum
- Hemorrhagic eruption
- Vaginitis
- Porphyria
- Impaired renal function
- Hemolytic uremic syndrome
- Acne
- Changes in libido
- Colitis
- Budd-Chiari Syndrome

OVERDOSAGE

Serious ill effects have not been reported following acute ingestion of large doses of oral contraceptives by young children. Overdosage may cause nausea and withdrawal bleeding may occur in females.

NON-CONTRACEPTIVE HEALTH BENEFITS

The following non-contraceptive health benefits related to the use of combination oral contraceptives are supported by epidemiological studies which largely utilized oral contraceptive formulations containing estrogen doses exceeding 0.035 mg of ethinyl estradiol or 0.05 mg mestranol^73–78.

Effects on menses:

- increased menstrual cycle regularity
- decreased blood loss and decreased incidence of iron deficiency anemia
- decreased incidence of dysmenorrhea

Effects related to inhibition of ovulation:

- decreased incidence of functional ovarian cysts
- decreased incidence of ectopic pregnancies

Other effects:

- decreased incidence of fibroadenomas and fibrocystic disease of the breast
- decreased incidence of acute pelvic inflammatory disease
- decreased incidence of endometrial cancer
- decreased incidence of ovarian cancer

DOSAGE AND ADMINISTRATION

Oral Contraception

To achieve maximum contraceptive effectiveness, ORTHO TRI-CYCLEN® Tablets and ORTHO-CYCLEN® Tablets must be taken exactly as directed and at intervals not exceeding 24 hours. The possibility of ovulation and conception prior to initiation of medication should be considered. ORTHO TRI-CYCLEN and ORTHO-CYCLEN are available in the DIALPAK® Tablet Dispenser which is preset for a Sunday Start. Day 1 Start is also provided.

Sunday Start

When taking ORTHO TRI-CYCLEN® and ORTHO-CYCLEN® the first tablet should be taken on the first Sunday after menstruation begins. If period begins on Sunday, the first tablet should be taken that day. Take one active tablet daily for 21 days followed by one dark green inactive tablet daily for 7 days. After 28 tablets have been taken, a new course is started the next day (Sunday). For the first cycle of a Sunday Start regimen, another method of contraception should be used until after the first 7 consecutive days of administration.

If the patient misses one (1) active tablet in Weeks 1, 2, or 3, the tablet should be taken as soon as she remembers. If the patient misses two (2) active tablets in Week 1 or Week 2, the patient should take two (2) tablets the day she remembers and two (2) tablets the next day; and then continue taking one (1) tablet a day until she finishes the pack. The patient should be instructed to use a back-up method of birth control such as condoms or spermicide if she has sex in the seven (7) days after missing pills. If the patient misses two (2) active tablets in the third week or misses three (3) or more active tablets in a row, the patient should continue taking one tablet every day until Sunday. On Sunday the patient should throw out the rest of the pack and start a new pack that same day. The patient should be instructed to use a back-up method of birth control if she has sex in the seven (7) days after missing pills.

Complete instructions to facilitate patient counseling on proper pill usage may be found in the Detailed Patient Labeling ("How to Take the Pill" section).

Day 1 Start

The dosage of ORTHO TRI-CYCLEN® and ORTHO-CYCLEN® , for the initial cycle of therapy is one active tablet administered daily from the 1st day through the 21st day of the menstrual cycle, counting the first day of menstrual flow as "Day 1" followed by one dark green inactive tablet daily for 7 days. Tablets are taken without interruption for 28 days. After 28 tablets have been taken, a new course is started the next day.

If the patient misses one (1) active tablet in Weeks 1, 2, or 3, the tablet should be taken as soon as she remembers. If the patient misses two (2) active tablets in Week 1 or Week 2, the patient should take two (2) tablets the day she remembers and two (2) tablets the next day; and then continue taking one (1) tablet a day until she finishes the pack. The patient should be instructed to use a back-up method of birth control such as condoms or spermicide if she has sex in the seven (7) days after missing pills. If the patient misses two (2) active tablets in the third week or misses three (3) or more active tablets in a row, the patient should throw out the rest of the pack and start a new pack that same day. The patient should be instructed to use a back-up method of birth control if she has sex in the seven (7) days after missing pills.

Complete instructions to facilitate patient counseling on proper pill usage may be found in the Detailed Patient Labeling ("How to Take the Pill" section).

The use of ORTHO TRI-CYCLEN and ORTHO-CYCLEN for contraception may be initiated 4 weeks postpartum in women who elect not to breast feed. When the tablets are administered during the postpartum period, the increased risk of thromboembolic disease associated with the postpartum period must be considered. (See CONTRAINDICATIONS and WARNINGS concerning thromboembolic disease. See also PRECAUTIONS for "Nursing Mothers.") The possibility of ovulation and conception prior to initiation of medication should be considered.

(See Discussion of Dose-Related Risk of Vascular Disease from Oral Contraceptives.)

ADDITIONAL INSTRUCTIONS

Breakthrough bleeding, spotting, and amenorrhea are frequent reasons for patients discontinuing oral contraceptives. In breakthrough bleeding, as in all cases of irregular bleeding from the vagina, nonfunctional causes should be borne in mind. In undiagnosed persistent or recurrent abnormal bleeding from the vagina, adequate diagnostic measures are indicated to rule out pregnancy or malignancy. If pathology has been excluded, time or a change to another formulation may solve the problem. Changing to an oral contraceptive with a higher estrogen content, while potentially useful in minimizing menstrual irregularity, should be done only if necessary since this may increase the risk of thromboembolic disease.

Use of oral contraceptives in the event of a missed menstrual period:

1. If the patient has not adhered to the prescribed schedule, the possibility of pregnancy should be considered at the time of the first missed period and oral contraceptive use should be discontinued if pregnancy is confirmed.
2. If the patient has adhered to the prescribed regimen and misses two consecutive periods, pregnancy should be ruled out.

ACNE

The timing of initiation of dosing with ORTHO TRI-CYCLEN® for acne should follow the guidelines for use of ORTHO TRI-CYCLEN as an oral contraceptive. Consult the DOSAGE AND ADMINISTRATION section for oral contraceptives. The dosage regimen for ORTHO TRI-CYCLEN for treatment of facial acne, as available in a DIALPAK® Tablet Dispenser, utilizes a 21-day active and a 7-day placebo schedule. Take one active tablet daily for 21 days followed by one dark green inactive tablet for 7 days. After 28 tablets have been taken, a new course is started the next day.

HOW SUPPLIED

ORTHO TRI-CYCLEN® Tablets are available in a DIALPAK® Tablet Dispenser (NDC 54868-4093-0) containing 28 tablets. Each white tablet contains 0.180 mg of the progestational compound, norgestimate, together with 0.035 mg of the estrogenic compound, ethinyl estradiol. Each light blue tablet contains 0.215 mg of the progestational compound, norgestimate, together with 0.035 mg of the estrogenic compound, ethinyl estradiol. Each blue tablet contains 0.250 mg of the progestational compound, norgestimate, together with 0.035 mg of the estrogenic compound, ethinyl estradiol. Each dark green tablet contains inert ingredients.

0.180/0.035 mg tablets - White, round, biconvex, coated tablet imprinted "O 180" on one side and "35" on the other side of the tablet.

0.215/0.035 mg tablets - Light blue, round, biconvex, coated tablet imprinted "O 215" on one side and "35" on the other side of the tablet.

0.250/0.035 mg tablets - Blue, round, biconvex, coated tablet imprinted "O 250" on one side and "35" on the other side of the tablet.

Each dark green reminder pill is a round, biconvex, coated tablet imprinted "O-M" on one side and "P" on the other side.

ORTHO TRI-CYCLEN® Tablets are available for clinic usage in a VERIDATE® Tablet Dispenser (unfilled) and VERIDATE Refills.

Keep out of reach of children.

Store at 25°C (77°F); excursions permitted to 15–30°C (59–86°F).

Protect from light.

REFERENCES

1. Trussel J. Contraceptive efficacy. In Hatcher RA, Trussel J, Stewart F, Cates W, Stewart GK, Kowal D, Guest F, Contraceptive Technology: Seventeenth Revised Edition. New York NY: Irvington Publishers, 1998, in press
2. Stadel BV, Oral contraceptives and cardiovascular disease. (Pt.1). N Engl J Med 1981; 305:612–618.
3. Stadel BV, Oral contraceptives and cardiovascular disease. (Pt.2). N Engl J Med 1981; 305:672–677.
4. Adam SA, Thorogood M. Oral contraception and myocardial infarction revisited: the effects of new preparations and prescribing patterns. Br J Obstet Gynaecol 1981; 88:838–845.
5. Mann Jl, Inman WH. Oral contraceptives and death from myocardial infarction. Br Med J 1975; 2(5965):245–248.
6. Mann Jl, Vessey MP, Thorogood M, Doll R. Myocardial infarction in young women with special reference to oral contraceptive practice. Br Med J 1975; 2(5956):241–245.
7. Royal College of General Practitioners' Oral Contraception Study: Further analyses of mortality in oral contraceptive users. Lancet 1981; 1:541–546.
8. Slone D, Shapiro S, Kaufman DW, Rosenberg L, Miettinen OS, Stolley PD. Risk of myocardial infarction in relation to current and discontinued use of oral contraceptives. N Engl J Med 1981:305:420–424.
9. Vessey MP. Female hormones and vascular disease-an epidemiological overview. Br J Fam Plann 1980; 6(Supplement): 1–12.
10. Russell-Briefel RG, Ezzati TM, Fulwood R, Perlman JA, Murphy RS. Cardiovascular risk status and oral contraceptive use, United States, 1976–80. Prevent Med 1986; 15:352–362.
11. Goldbaum GM, Kendrick JS, Hogelin GC, Gentry EM. The relative impact of smoking and oral contraceptive use on women in the United States. JAMA 1987; 258:1339–1342.
12. Layde PM, Beral V. Further analyses of mortality in oral contraceptive users; Royal College of General Practitioners' Oral Contraception Study. (Table 5) Lancet 1981; 1:541–546.
13. Knopp RH. Arteriosclerosis risk: the roles of oral contraceptives and postmenopausal estrogens. J Reprod Med 1986; 31(9) (Supplement):913–921.
14. Krauss RM, Roy S, Mishell DR, Casagrande J, Pike MC. Effects of two low-dose oral contraceptives on serum lipids and lipoproteins: Differential changes in high-density lipoproteins subclasses. Am J Obstet 1983; 145:446–452.
15. Wahl P, Walden C, Knopp R, Hoover J, Wallace R, Heiss G, Rifkind B. Effect of estrogen/progestin potency on lipid/lipoprotein cholesterol. N Engl J Med 1983; 308:862–867.
16. Wynn V, Niththyananthan R. The effect of progestin in combined oral contraceptives on serum lipids with special reference to high density lipoproteins. Am J Obstet Gynecol 1982;142:766–771.
17. Wynn V, Godsland I. Effects of oral contraceptives on carbohydrate metabolism. J Reprod Med 1986;31(9)(Supplement):892–897.
18. LaRosa JC. Atherosclerotic risk factors in cardiovascular disease. J Reprod Med 1986;31(9)(Supplement):906–912.
19. Inman WH, Vessey MP. Investigation of death from pulmonary, coronary, and cerebral thrombosis and embolism in women of child-bearing age. Br Med J 1968;2(5599):193–199.
20. Maguire MG, Tonascia J, Sartwell PE, Stolley PD, Tockman MS. Increased risk of thrombosis due to oral contraceptives: a further report. Am J Epidemiol 1979;110(2):188–195.
21. Petitti DB, Wingerd J, Pellegrin F, Ramacharan S. Risk of vascular disease in women: smoking, oral contraceptives, noncontraceptive estrogens, and other factors. JAMA 1979;242:1150–1154.
22. Vessey MP, Doll R, Investigation of relation between use of oral contraceptives and thromboembolic disease. Br Med J 1968;2(5599):199–205.
23. Vessey MP, Doll R. Investigation of relation between use of oral contraceptives and thromboembolic disease. A further report. Br Med J 1969; 2(5658):651–657.
24. Porter JB, Hunter JR, Danielson DA, Jick H, Stergachis A. Oral contraceptives and non-fatal vascular disease-recent experience. Obstet Gynecol 1982;59(3):299–302.
25. Vessey M, Doll R, Peto R, Johnson B, Wiggins P. A long-term follow-up study of women using different methods of contraception: an interim report. J Biosocial Sci 1976;8:375–427.
26. Royal College of General Practitioners: Oral Contraceptives, venous thrombosis, and varicose veins. J Royal Coll Gen Pract 1978; 28:393–399.
27. Collaborative Group for the Study of Stroke in Young Women: Oral contraception and increased risk of cerebral ischemia or thrombosis. N Engl J Med 1973;288:871–878.
28. Petitti DB, Wingerd J. Use of oral contraceptives, cigarette smoking, and risk of subarachnoid hemorrhage. Lancet 1978;2:234–236.
29. Inman WH. Oral contraceptives and fatal subarachnoid hemorrhage. Br Med J 1979:2(6203):1468–1470.
30. Collaborative Group for the Study of Stroke in Young Women: Oral Contraceptives and stroke in young women: associated risk factors. JAMA 1975; 231:718–722.
31. Inman WH, Vessey MP, Westerholm B, Engelund A. Thromboembolic disease and the steroidal content of oral contraceptives. A report to the Committee on Safety of Drugs. Br Med J 1970;2:203–209.
32. Meade TW, Greenberg G, Thompson SG. Progestogens and cardiovascular reactions associated with oral contraceptives and a comparison of the safety of 50- and 35-mcg oestrogen preparations. Br Med J 1980;280(6224):1157–1161.
33. Kay CR. Progestogens and arterial disease-evidence from the Royal College of General Practitioners' Study. Am J Obstet Gynecol 1982;142:762–765.
34. Royal College of General Practitioners: Incidence of arterial disease among oral contraceptive users. J Royal Coll Gen Pract 1983;33:75–82.
35. Ory HW. Mortality associated with fertility and fertility control: 1983. Family Planning Perspectives 1983;15:50–56.
36. The Cancer and Steroid Hormone Study of the Centers for Disease Control and the National Institute of Child Health and Human Development: Oral contraceptive use and the risk of breast cancer. N Engl J Med 1986;315:405–411.
37. Pike MC, Henderson BE, Krailo MD, Duke A, Roy S. Breast cancer in young women and use of oral contraceptives: possible modifying effect of formulation and age at use. Lancet 1983;2:926–929.
38. Paul C, Skegg DG, Spears GFS, Kaldor JM. Oral contraceptives and breast cancer: A national study. Br Med J 1986; 293:723–725.
39. Miller DR, Rosenberg L, Kaufman DW, Schottenfeld D, Stolley PD, Shapiro S. Breast cancer risk in relation to early oral contraceptive use. Obstet Gynecol 1986;68:863–868.
40. Olsson H, Olsson ML, Moller TR, Ranstam J, Holm P. Oral contraceptive use and breast cancer in young women in Sweden (letter). Lancet 1985; 1(8431):748–749.
41. McPherson K, Vessey M, Neil A, Doll R, Jones L, Roberts M. Early contraceptive use and breast cancer: Results of another case-control study. Br J Cancer 1987; 56:653–660.
42. Huggins GR, Zucker PF. Oral contraceptives and neoplasia; 1987 update. Fertil Steril 1987; 47:733–761.
43. McPherson K, Drife JO. The pill and breast cancer: why the uncertainty? Br Med J 1986; 293:709–710.
44. Shapiro S. Oral contraceptives-time to take stock. N Engl J Med 1987; 315:450–451.
45. Ory H, Naib Z, Conger SB, Hatcher RA, Tyler CW. Contraceptive choice and prevalence of cervical dysplasia and carcinoma in situ. Am J Obstet Gynecol 1976; 124:573–577.
46. Vessey MP, Lawless M, McPherson K, Yeates D. Neoplasia of the cervix uteri and contraception: a possible adverse effect of the pill. Lancet 1983; 2:930.
47. Brinton LA, Huggins GR, Lehman HF, Malli K, Savitz DA, Trapido E, Rosenthal J, Hoover R. Long term use of oral contraceptives and risk of invasive cervical cancer. Int J Cancer 1986; 38:339–344.
48. WHO Collaborative Study of Neoplasia and Steroid Contraceptives: Invasive cervical cancer and combined oral contraceptives. Br Med J 1985; 290:961–965.
49. Rooks JB, Ory HW, Ishak KG, Strauss LT, Greenspan JR, Hill AP, Tyler CW. Epidemiology of hepatocellular adenoma: the role of oral contraceptive use. JAMA 1979; 242:644–648.
50. Bein NN, Goldsmith HS. Recurrent massive hemorrhage from benign hepatic tumors secondary to oral contraceptives. Br J Surg 1977; 64:433–435.
51. Klatskin G. Hepatic tumors: possible relationship to use of oral contraceptives. Gastroenterology 1977; 73:386–394.
52. Henderson BE, Preston-Martin S, Edmondson HA, Peters RL, Pike MC. Hepatocellular carcinoma and oral contraceptives. Br J Cancer 1983;48:437–440.
53. Neuberger J, Forman D, Doll R, Williams R. Oral contraceptives and hepatocellular carcinoma. Br Med J 1986; 292:1355–1357.
54. Forman D, Vincent TJ, Doll R, Cancer of the liver and oral contraceptives. Br Med J 1986; 292:1357–1361.
55. Harlap S, Eldor J. Births following oral contraceptive failures. Obstet Gynecol 1980; 55:447–452.
56. Savolainen E, Saksela E, Saxen L. Teratogenic hazards of oral contraceptives analyzed in a national malformation register. Am J Obstet Gynecol 1981: 140:521–524.
57. Janerich DT, Piper JM, Glebatis DM. Oral contraceptives and birth defects. Am J Epidemiol 1980; 112:73–79.
58. Ferencz C, Matanoski GM, Wilson PD, Rubin JD, Neill CA, Gutberlet R. Maternal hormone therapy and congenital heart disease. Teratology 1980; 21:225–239.
59. Rothman KJ, Fyler DC, Goldblatt A, Kreidberg MB. Exogenous hormones and other drug exposures of children with congenital heart disease. Am J Epidemiol 1979; 109:433–439.
60. Boston Collaborative Drug Surveillance Program: Oral contraceptives and venous thromboembolic disease, surgically confirmed gallbladder disease, and breast tumors. Lancet 1973; 1:1399–1404.
61. Royal College of General Practitioners: Oral contraceptives and health. New York, Pittman 1974.
62. Layde PM, Vessey MP, Yeates D. Risk of gallbladder disease: a cohort study of young women attending family planning clinics. J Epidemiol Community Health 1982; 36:274–278.
63. Rome Group for Epidemiology and Prevention of Cholelithiasis (GREPCO): Prevalence of gallstone disease in an Italian adult female population. Am J Epidemiol 1984; 119:796–805.
64. Storm BL, Tamragouri RT, Morse ML, Lazar EL, West SL, Stolley PD, Jones JK. Oral contraceptives and other risk factors for gallbladder disease. Clin Pharmacol Ther 1986; 39:335–341.
65. Wynn V, Adams PW, Godsland IF, Melrose J, Niththyananthan R, Oakley NW, Seedj A. Comparison of effects of different combined oral contraceptive formulations on carbohydrate and lipid metabolism. Lancet 1979; 1:1045–1049.
66. Wynn V. Effect of progesterone and progestins on carbohydrate metabolism. In: Progesterone and Progestin. Bardin CW, Milgrom E, Mauvis-Jarvis P. eds. New York, Raven Press 1983; pp. 395–410.
67. Perlman JA, Roussell-Briefel RG, Ezzati TM, Lieberknecht G. Oral glucose tolerance and the potency of oral contraceptive progestogens. J Chronic Dis 1985;38:857–864.
68. Royal College of General Practitioners' Oral Contraception Study: Effect on hypertension and benign breast disease of progestogen component in combined oral contraceptives. Lancet 1977; 1:624.
69. Fisch IR, Frank J. Oral contraceptives and blood pressure. JAMA 1977; 237:2499–2503.
70. Laragh AJ. Oral contraceptive induced hypertension-nine years later. Am J Obstet Gynecol 1976; 126:141–147.
71. Ramcharan S, Peritz E, Pellegrin FA, Williams WT. Incidence of hypertension in the Walnut Creek Contraceptive Drug Study cohort: In: Pharmacology of steroid contraceptive drugs. Garattini S, Berendes HW. Eds. New York, Raven Press, 1977; pp. 277–288, (Monographs of the Mario Negri Institute for Pharmacological Research Milan.)
72. Stockley I. Interactions with oral contraceptives. J Pharm 1976;216:140–143.
73. The Cancer and Steriod Hormone Study of the Centers for Disease Control and the National Institute of Child Health and Human Development: Oral contraceptive use and the risk of ovarian cancer. JAMA 1983; 249:1596–1599.
74. The Cancer and Steroid Hormone Study of the Centers for Disease Control and the National Institute of Child Health and Human Development: Combination oral contraceptive use and the risk of endometrial cancer. JAMA 1987; 257:796–800.
75. Ory HW. Functional ovarian cysts and oral contraceptives: negative association confirmed surgically. JAMA 1974; 228:68–69.
76. Ory HW, Cole P, MacMahon B, Hoover R. Oral contraceptives and reduced risk of benign breast disease. N Engl J Med 1976; 294:419–422.
77. Ory HW. The noncontraceptive health benefits from oral contraceptive use. Fam Plann Perspect 1982; 14:182–184.
78. Ory HW, Forrest JD, Lincoln R. Making choices: Evaluating the health risks and benefits of birth control methods. New York, The Alan Guttmacher Institute, 1983; p.1.
79. Schlesselman J, Stadel BV, Murray P, Lai S. Breast cancer in relation to early use of oral contraceptives. JAMA 1988; 259:1828–1833.
80. Hennekens CH, Speizer FE, Lipnick RJ, Rosner B, Bain C, Belanger C, Stampfer MJ, Willett W, Peto R. A case-control study of oral contraceptive use and breast cancer. JNCI 1984; 72:39–42.
81. LaVecchia C, Decarli A, Fasoli M, Franceschi S, Gentile A, Negri E, Parazzini F, Tognoni G. Oral contraceptives and cancers of the breast and of the female genital tract. Interim results from a case-control study. Br J Cancer 1986; 54:311–317.
82. Meirik O, Lund E, Adami H, Bergstrom R, Christoffersen T, Bergsjo P. Oral contraceptive use and breast cancer in young women. A Joint National Case-control study in Sweden and Norway. Lancet 1986; 11:650–654.
83. Kay CR, Hannaford PC. Breast cancer and the pill-A further report from the Royal College of General Practitioners' oral contraception study. Br J Cancer 1988;58:675–680.
84. Stadel BV, Lai S, Schlesselman JJ, Murray P. Oral contraceptives and premenopausal breast cancer in nulliparous women. Contraception 1988; 38:287–299.
85. Miller DR, Rosenberg L, Kaufman DW, Stolley P, Warshauer ME, Shapiro S. Breast cancer before age 45 and oral contraceptive use: New Findings. Am J Epidemiol 1989; 129:269–280.
86. The UK National Case-Control Study Group, Oral contraceptive use and breast cancer risk in young women. Lancet 1989; 1:973–982.
87. Schlesselman JJ. Cancer of the breast and reproductive tract in relation to use of oral contraceptives. Contraception 1989; 40:1–38.
88. Vessey MP, McPherson K, Villard-Mackintosh L, Yeates D. Oral contraceptives and breast cancer: latest findings in a large cohort study. Br J Cancer 1989; 59:613–617.
89. Jick SS, Walker AM, Stergachis A, Jick H. Oral contraceptives and breast cancer. Br J Cancer 1989; 59:618–621.
90. Anderson FD, Selectivity and minimal androgenicity of norgestimate in monophasic and triphasic oral contraceptives. Acta Obstet Gynecol Scand 1992; 156 (Supplement):15–21.
91. Chapdelaine A, Desmaris J-L, Derman RJ. Clinical evidence of minimal androgenic activity of norgestimate. Int J Fertil 1989; 34(51):347–352.
92. Phillips A, Demarest K, Hahn DW, Wong F, McGuire JL. Progestational and androgenic receptor binding affinities and in vivo activities of norgestimate and other progestins. Contraception 1989; 41(4):399–409.
93. Phillips A, Hahn DW, Klimek S, McGuire JL. A comparison of the potencies and activities of progestogens used in contraceptives. Contraception 1987; 36(2):181–192.
94. Janaud A, Rouffy J, Upmalis D, Dain M-P. A comparison study of lipid and androgen metabolism with triphasic oral contraceptive formulations containing norgestimate or levonorgestrel Acta Obstet Gynecol Scand 1992; 156 (Supplement):34–38.
95. Collaborative Group on Hormonal Factors in Breast Cancer. Breast cancer and hormonal contraceptives: collaborative reanalysis of individual data on 53 297 women with breast cancer and 100 239 women without breast cancer from 54 epidemiological studies. Lancet 1996; 347:1713–1727.
96. Palmer JR, Rosenberg L, Kaufman DW, Warshauer ME, Stolley P, Shapiro S. Oral Contraceptive Use and Liver Cancer. Am J Epidemiol 1989;130:878–882.
97. Lewis M, Spitzer WO, Heinemann LAJ, MacRae KD, Bruppacher R, Thorogood M on behalf of Transnational Research Group on Oral Contraceptives and Health of Young Women. Third generation oral contraceptives and risk of myocardial infarction: an international case-control study. Br Med J, 1996;312:88–90.
98. Improving access to quality care in family planning: Medical eligibility criteria for contraceptive use. Geneva, WHO, Family and Reproductive Health, 1996.
99. Bork K, Fischer B, DeWald G. Recurrent episodes of skin angioedema and severe attacks of abdominal pain induced by oral contraceptives or hormone replacement therapy. Am J Med 2003;114:294–298.
100. Van Giersbergen PLM, Halabi A, Dingemanse J. Pharmacokinetic interaction between bosentan and the oral contraceptives norethisterone and ethinyl estradiol. Int J Clin Pharmacol Ther 2006;44(3):113–118.
101. Christensen J, Petrenaite V, Atterman J, et al. Oral contraceptives induce lamotrigine metabolism: evidence from a double-blind, placebo-controlled trial. Epilepsia 2007;48(3):484–489.

BRIEF SUMMARY PATIENT PACKAGE INSERT

This product (like all oral contraceptives) does not protect against HIV infection (AIDS) and other sexually transmitted diseases.

Oral contraceptives, also known as "birth control pills" or "the pill," are taken to prevent pregnancy. When taken correctly to prevent pregnancy, oral contraceptives have a failure rate of approximately 1% per year (1 pregnancy per 100 women per year of use) when used without missing any pills. The typical failure rate is approximately 5% per year (5 pregnancies per 100 women per year of use) when women who miss pills are included. For most women oral contraceptives are also free of serious or unpleasant side effects. However, forgetting to take pills considerably increases the chances of pregnancy.

ORTHO TRI-CYCLEN® may also be taken to treat moderate acne in females at least 15 years of age, who have started having menstrual periods, are able to take the pill and want to use the pill for birth control.

For the majority of women, oral contraceptives can be taken safely. But there are some women who are at high risk of developing certain serious diseases that can be fatal or may cause temporary or permanent disability. The risks associated with taking oral contraceptives increase significantly if you:

- smoke
- have high blood pressure, diabetes, high cholesterol
- have or have had clotting disorders, heart attack, stroke, angina pectoris, cancer of the breast or sex organs, jaundice or malignant or benign liver tumors

Although cardiovascular disease risks may be increased with oral contraceptive use after age 40 in healthy, non-smoking women (even with the newer low-dose formulations), there are also greater potential health risks associated with pregnancy in older women.

You should not take the pill if you suspect you are pregnant or have unexplained vaginal bleeding.

BOXED WARNING

Cigarette smoking increases the risk of serious cardiovascular side effects from oral contraceptive use. This risk increases with age and with heavy smoking (15 or more cigarettes per day) and is quite marked in women over 35 years of age. Women who use oral contraceptives are strongly advised not to smoke.

Most side effects of the pill are not serious. The most common such effects are nausea, vomiting, bleeding between menstrual periods, weight gain, breast tenderness, and difficulty wearing contact lenses. These side effects, especially nausea and vomiting, may subside within the first three months of use.

The serious side effects of the pill occur very infrequently, especially if you are in good health and are young. However, you should know that the following medical conditions have been associated with or made worse by the pill:

1. Blood clots in the legs (thrombophlebitis), lungs (pulmonary embolism), stoppage or rupture of a blood vessel in the brain (stroke), blockage of blood vessels in the heart (heart attack or angina pectoris) or other organs of the body. As mentioned above, smoking increases the risk of heart attacks and strokes and subsequent serious medical consequences.
2. In rare cases, oral contraceptives can cause benign but dangerous liver tumors. These benign liver tumors can rupture and cause fatal internal bleeding. In addition, some studies report an increased risk of developing liver cancer. However, liver cancers are rare.
3. High blood pressure, although blood pressure usually returns to normal when the pill is stopped.

The symptoms associated with these serious side effects are discussed in the detailed leaflet given to you with your supply of pills. Notify your healthcare professional if you notice any unusual physical disturbances while taking the pill. In addition, drugs such as rifampin, as well as some anticonvulsants and some antibiotics may decrease oral contraceptive effectiveness.

Oral contraceptives may interact with lamotrigine (LAMICTAL®), an anticonvulsant used for epilepsy. This may increase the risk of seizures so your healthcare professional may need to adjust the dose of lamotrigine.

Various studies give conflicting reports on the relationship between breast cancer and oral contraceptive use. Oral contraceptive use may slightly increase your chance of having breast cancer diagnosed, particularly after using hormonal contraceptives at a younger age. After you stop using hormonal contraceptives, the chances of having breast cancer diagnosed begin to go back down. You should have regular breast examinations by a healthcare professional and examine your own breasts monthly. Tell your healthcare professional if you have a family history of breast cancer or if you have had breast nodules or an abnormal mammogram. Women who currently have or have had breast cancer should not use oral contraceptives because breast cancer is usually a hormone-sensitive tumor.

Some studies have found an increase in the incidence of cancer of the cervix in women who use oral contraceptives. However, this finding may be related to factors other than the use of oral contraceptives. There is insufficient evidence to rule out the possibility that the pill may cause such cancers.

Taking the combination pill provides some important non-contraceptive benefits. These include less painful menstruation, less menstrual blood loss and anemia, fewer pelvic infections, and fewer cancers of the ovary and the lining of the uterus.

Be sure to discuss any medical condition you may have with your healthcare professional. Your healthcare professional will take a medical and family history before prescribing oral contraceptives and will examine you. The physical examination may be delayed to another time if you request it and the healthcare professional believes that it is a good medical practice to postpone it. You should be reexamined at least once a year while taking oral contraceptives. Your pharmacist should have given you the detailed patient information labeling which gives you further information which you should read and discuss with your healthcare professional.

HOW TO TAKE THE PILL

IMPORTANT POINTS TO REMEMBER

BEFORE YOU START TAKING YOUR PILLS:

1. BE SURE TO READ THESE DIRECTIONS:
  Before you start taking your pills.
  Anytime you are not sure what to do.
2. THE RIGHT WAY TO TAKE THE PILL IS TO TAKE ONE PILL EVERY DAY AT THE SAME TIME.
  If you miss pills you could get pregnant. This includes starting the pack late.
  The more pills you miss, the more likely you are to get pregnant.
3. MANY WOMEN HAVE SPOTTING OR LIGHT BLEEDING, OR MAY FEEL SICK TO THEIR STOMACH DURING THE FIRST 1–3 PACKS OF PILLS. If you feel sick to your stomach or have spotting or light bleeding, do not stop taking the pill. The problem will usually go away. If it doesn't go away, check with your healthcare professional.
4. MISSING PILLS CAN ALSO CAUSE SPOTTING OR LIGHT BLEEDING, even when you make up these missed pills.
  On the days you take 2 pills to make up for missed pills, you could also feel a little sick to your stomach.
5. IF YOU HAVE VOMITING OR DIARRHEA, OR IF YOU TAKE SOME MEDICINES, including some antibiotics, your pills may not work as well.
  Use a back-up method (such as condoms or spermicide) until you check with your healthcare professional.
6. IF YOU HAVE TROUBLE REMEMBERING TO TAKE THE PILL, talk to your healthcare professional about how to make pill-taking easier or about using another method of birth control.
7. IF YOU HAVE ANY QUESTIONS OR ARE UNSURE ABOUT THE INFORMATION IN THIS LEAFLET, call your healthcare professional.

BEFORE YOU START TAKING YOUR PILLS

1. DECIDE WHAT TIME OF DAY YOU WANT TO TAKE YOUR PILL.
  It is important to take it at about the same time every day.
2. LOOK AT YOUR PILL PACK
  The pill pack has 21 "active" pills (with hormones) to take for 3 weeks. This is followed by 1 week of "reminder" dark green pills (without hormones).
  ORTHO TRI-CYCLEN®: There are 7 white "active" pills, 7 light blue "active" pills, 7 blue "active" pills, and 7 dark green "reminder" pills.
  ORTHO-CYCLEN®: There are 21 blue "active" pills, and 7 dark green "reminder" pills.
3. ALSO FIND:
  1) where on the pack to start taking pills,
  2) in what order to take the pills.
4. BE SURE YOU HAVE READY AT ALL TIMES:
  ANOTHER KIND OF BIRTH CONTROL (such as condoms or spermicide) to use as a back-up method in case you miss pills.
  AN EXTRA, FULL PILL PACK.

WHEN TO START THE FIRST PACK OF PILLS

You have a choice of which day to start taking your first pack of pills. ORTHO TRI-CYCLEN® and ORTHO-CYCLEN® are available in the DIALPAK® Tablet Dispenser which is preset for a Sunday Start. Day 1 Start is also provided. Decide with your healthcare professional which is the best day for you. Pick a time of day which will be easy to remember.

Sunday Start:

ORTHO TRI-CYCLEN®: Take the first white "active" pill of the first pack on the Sunday after your period starts, even if you are still bleeding. If your period begins on Sunday, start the pack that same day.

ORTHO-CYCLEN®: Take the first blue "active" pill of the first pack on the Sunday after your period starts, even if you are still bleeding. If your period begins on Sunday, start the pack that same day.

Use another method of birth control such as condoms or spermicide as a back-up method if you have sex anytime from the Sunday you start your first pack until the next Sunday (7 days).

Day 1 Start:

ORTHO TRI-CYCLEN®: Take the first white "active" pill of the first pack during the first 24 hours of your period.

ORTHO-CYCLEN®: Take the first blue "active" pill of the first pack during the first 24 hours of your period.

You will not need to use a back-up method of birth control, since you are starting the pill at the beginning of your period.

WHAT TO DO DURING THE MONTH

1. TAKE ONE PILL AT THE SAME TIME EVERY DAY UNTIL THE PACK IS EMPTY.
  Do not skip pills even if you are spotting or bleeding between monthly periods or feel sick to your stomach (nausea).
  Do not skip pills even if you do not have sex very often.
2. WHEN YOU FINISH A PACK OR SWITCH YOUR BRAND OF PILLS:
  Start the next pack on the day after your last "reminder" pill. Do not wait any days between packs.

WHAT TO DO IF YOU MISS PILLS

ORTHO TRI-CYCLEN®:

If you MISS 1 white, light blue or blue "active" pill:

1. Take it as soon as you remember. Take the next pill at your regular time. This means you may take 2 pills in 1 day.
2. You do not need to use a back-up birth control method if you have sex.

If you MISS 2 white or light blue "active" pills in a row in WEEK 1 OR WEEK 2 of your pack:

1. Take 2 pills on the day you remember and 2 pills the next day.
2. Then take 1 pill a day until you finish the pack.
3. You COULD BECOME PREGNANT if you have sex in the 7 days after you miss pills. You MUST use another birth control method (such as condoms or spermicide) as a back-up method for those 7 days.

If you MISS 2 blue "active" pills in a row in THE 3RD WEEK:

1. If you are a Sunday Starter:
  Keep taking 1 pill every day until Sunday. On Sunday, THROW OUT the rest of the pack and start a new pack of pills that same day.
  If you are a Day 1 Starter:
  THROW OUT the rest of the pill pack and start a new pack that same day.
2. You may not have your period this month but this is expected. However, if you miss your period 2 months in a row, call your healthcare professional because you might be pregnant.
3. You COULD BECOME PREGNANT if you have sex in the 7 days after you miss pills. You MUST use another birth control method (such as condoms or spermicide) as a back-up method for those 7 days.

If you MISS 3 OR MORE white, light blue or blue "active" pills in a row (during the first 3 weeks):

1. If you are a Sunday Starter:
  Keep taking 1 pill every day until Sunday. On Sunday, THROW OUT the rest of the pack and start a new pack of pills that same day.
  If you are a Day 1 Starter:
  THROW OUT the rest of the pill pack and start a new pack that same day.
2. You may not have your period this month but this is expected. However, if you miss your period 2 months in a row, call your healthcare professional because you might be pregnant.
3. You COULD BECOME PREGNANT if you have sex in the 7 days after you miss pills. You MUST use another birth control method (such as condoms or spermicide) as a back-up method for those 7 days.

ORTHO-CYCLEN®:

If you MISS 1 blue "active" pill:

1. Take it as soon as you remember. Take the next pill at your regular time. This means you may take 2 pills in 1 day.
2. You do not need to use a back-up birth control method if you have sex.

If you MISS 2 blue "active" pills in a row in WEEK 1 OR WEEK 2 of your pack:

1. Take 2 pills on the day you remember and 2 pills the next day.
2. Then take 1 pill a day until you finish the pack.
3. You COULD BECOME PREGNANT if you have sex in the 7 days after you miss pills. You MUST use another birth control method (such as condoms or spermicide) as a back-up method for those 7 days.

If you MISS 2 blue "active" pills in a row in THE 3RD WEEK:

1. If you are a Sunday Starter:
  Keep taking 1 pill every day until Sunday. On Sunday, THROW OUT the rest of the pack and start a new pack of pills that same day.
  If you are a Day 1 Starter:
  THROW OUT the rest of the pill pack and start a new pack that same day.
2. You may not have your period this month but this is expected. However, if you miss your period 2 months in a row, call your healthcare professional because you might be pregnant.
3. You COULD BECOME PREGNANT if you have sex in the 7 days after you miss pills. You MUST use another birth control method (such as condoms or spermicide) as a back-up method for those 7 days.

If you MISS 3 OR MORE blue "active" pills in a row (during the first 3 weeks):

1. If you are a Sunday Starter:
  Keep taking 1 pill every day until Sunday. On Sunday, THROW OUT the rest of the pack and start a new pack of pills that same day.
  If you are a Day 1 Starter:
  THROW OUT the rest of the pill pack and start a new pack that same day.
2. You may not have your period this month but this is expected. However, if you miss your period 2 months in a row, call your healthcare professional because you might be pregnant.
3. You COULD BECOME PREGNANT if you have sex in the 7 days after you miss pills. You MUST use another birth control method (such as condoms or spermicide) as a back-up method for those 7 days.

A REMINDER:

If you forget any of the 7 dark green "reminder" pills in Week 4:

THROW AWAY the pills you missed.

Keep taking 1 pill each day until the pack is empty.

You do not need a back-up method.

FINALLY, IF YOU ARE STILL NOT SURE WHAT TO DO ABOUT THE PILLS YOU HAVE MISSED:

Use a BACK-UP METHOD anytime you have sex.

KEEP TAKING ONE "ACTIVE" PILL EACH DAY until you can reach your healthcare professional.

DETAILED PATIENT LABELING

PLEASE NOTE: This labeling is revised from time to time as important new medical information becomes available. Therefore, please review this labeling carefully.

This product (like all oral contraceptives) does not protect against HIV infection (AIDS) and other sexually transmitted diseases.

ORTHO TRI-CYCLEN® Regimen

Each white tablet contains 0.180 mg norgestimate and 0.035 mg ethinyl estradiol. Each light blue tablet contains 0.215 mg norgestimate and 0.035 mg ethinyl estradiol. Each blue tablet contains 0.250 mg norgestimate and 0.035 mg ethinyl estradiol. Each dark green tablet contains inert ingredients.

ORTHO-CYCLEN® Regimen

Each blue tablet contains 0.250 mg norgestimate and 0.035 mg ethinyl estradiol. Each dark green tablet contains inert ingredients.

INTRODUCTION

Any woman who considers using oral contraceptives (the birth control pill or the pill) should understand the benefits and risks of using this form of birth control. This patient labeling will give you much of the information you will need to make this decision and will also help you determine if you are at risk of developing any of the serious side effects of the pill. It will tell you how to use the pill properly so that it will be as effective as possible. However, this labeling is not a replacement for a careful discussion between you and your healthcare professional. You should discuss the information provided in this labeling with him or her, both when you first start taking the pill and during your revisits. You should also follow your healthcare professional's advice with regard to regular check-ups while you are on the pill.

EFFECTIVENESS OF ORAL CONTRACEPTIVES FOR CONTRACEPTION

Oral contraceptives or "birth control pills" or "the pill" are used to prevent pregnancy and are more effective than most other non-surgical methods of birth control. When they are taken correctly without missing any pills, the chance of becoming pregnant is approximately 1% per year (1 pregnancy per 100 women per year of use). Typical failure rates, including women who do not always take the pill correctly, are approximately 5% per year (5 pregnancies per 100 women per year of use). The chance of becoming pregnant increases with each missed pill during a menstrual cycle.

In comparison, typical failure rates for other non-surgical methods of birth control during the first year of use are as follows:

Implant: <1% | Male sterilization: <1%
Injection: <1% | Cervical Cap with spermicides: 20 to 40%
IUD: 1 to 2% | Condom alone (male): 14%
Diaphragm with spermicides: 20% | Condom alone (female): 21%
Spermicides alone: 26% | Periodic abstinence: 25%
Vaginal sponge: 20 to 40% | Withdrawal: 19%
Female sterilization: <1% | No methods: 85%

ORTHO TRI-CYCLEN® may also be taken to treat moderate acne if all of the following are true:

- You have started having menstrual cycles
- You are at least 15 years old
- Your healthcare professional says it is safe for you to use the pill
- You want to use the pill for birth control

WHO SHOULD NOT TAKE ORAL CONTRACEPTIVES

BOXED WARNING

Cigarette smoking increases the risk of serious cardiovascular side effects from oral contraceptive use. This risk increases with age and with heavy smoking (15 or more cigarettes per day) and is quite marked in women over 35 years of age. Women who use oral contraceptives are strongly advised not to smoke.

Some women should not use the pill. For example, you should not take the pill if you have any of the following conditions:

- A history of heart attack or stroke
- Blood clots in the legs (thrombophlebitis), lungs (pulmonary embolism), or eyes
- A history of blood clots in the deep veins of your legs
- Chest pain (angina pectoris)
- Known or suspected breast cancer or cancer of the lining of the uterus, cervix or vagina
- Unexplained vaginal bleeding (until a diagnosis is reached by your healthcare professional)
- Yellowing of the whites of the eyes or of the skin (jaundice) during pregnancy or during previous use of the pill
- Liver tumor (benign or cancerous) or active liver disease
- Known or suspected pregnancy
- Valvular heart disease with complications
- Severe hypertension
- Diabetes with vascular involvement
- Headaches with focal neurological symptoms
- Major surgery with prolonged immobilization
- Hypersensitivity to any component of this product

Tell your healthcare professional if you have had any of these conditions. Your healthcare professional can recommend a safer method of birth control.

OTHER CONSIDERATIONS BEFORE TAKING ORAL CONTRACEPTIVES

Tell your healthcare professional if you have or have had:

- Breast nodules, fibrocystic disease of the breast, an abnormal breast x-ray or mammogram
- Diabetes
- Elevated cholesterol or triglycerides
- High blood pressure
- Migraine or other headaches or epilepsy
- Mental depression
- Gallbladder, liver, heart or kidney disease
- History of scanty or irregular menstrual periods

Women with any of these conditions should be checked often by their healthcare professional if they choose to use oral contraceptives.

Also, be sure to inform your healthcare professional if you smoke or are on any medications.

RISKS OF TAKING ORAL CONTRACEPTIVES

1. Risk of Developing Blood Clots

Blood clots and blockage of blood vessels are one of the most serious side effects of taking oral contraceptives and can cause death or serious disability. In particular, a clot in the legs can cause thrombophlebitis and a clot that travels to the lungs can cause a sudden blocking of the vessel carrying blood to the lungs. Rarely, clots occur in the blood vessels of the eye and may cause blindness, double vision, or impaired vision.

If you take oral contraceptives and need elective surgery, need to stay in bed for a prolonged illness or injury or have recently delivered a baby, you may be at risk of developing blood clots. You should consult your healthcare professional about stopping oral contraceptives four weeks before surgery and not taking oral contraceptives for two weeks after surgery or during bed rest. You should also not take oral contraceptives soon after delivery of a baby. It is advisable to wait for at least four weeks after delivery if you are not breast feeding. If you are breast feeding, you should wait until you have weaned your child before using the pill. (See also the section on Breast Feeding in General Precautions.)

The risk of circulatory disease in oral contraceptive users may be higher in users of high- dose pills and may be greater with longer duration of oral contraceptive use. In addition, some of these increased risks may continue for a number of years after stopping oral contraceptives. The risk of abnormal blood clotting increases with age in both users and nonusers of oral contraceptives, but the increased risk from the oral contraceptive appears to be present at all ages. For women aged 20 to 44 it is estimated that about 1 in 2,000 using oral contraceptives will be hospitalized each year because of abnormal clotting. Among nonusers in the same age group, about 1 in 20,000 would be hospitalized each year. For oral contraceptive users in general, it has been estimated that in women between the ages of 15 and 34 the risk of death due to a circulatory disorder is about 1 in 12,000 per year, whereas for nonusers the rate is about 1 in 50,000 per year. In the age group 35 to 44, the risk is estimated to be about 1 in 2,500 per year for oral contraceptive users and about 1 in 10,000 per year for nonusers.

2. Heart Attacks and Strokes

Oral contraceptives may increase the tendency to develop strokes (stoppage or rupture of blood vessels in the brain) and angina pectoris and heart attacks (blockage of blood vessels in the heart). Any of these conditions can cause death or serious disability.

Smoking greatly increases the possibility of suffering heart attacks and strokes. Furthermore, smoking and the use of oral contraceptives greatly increase the chances of developing and dying of heart disease.

3. Gallbladder Disease

Oral contraceptive users probably have a greater risk than nonusers of having gallbladder disease, although this risk may be related to pills containing high doses of estrogens.

4. Liver Tumors

In rare cases, oral contraceptives can cause benign but dangerous liver tumors. These benign liver tumors can rupture and cause fatal internal bleeding. In addition, some studies report an increased risk of developing liver cancer. However, liver cancers are rare.

5. Cancer of the Reproductive Organs and Breasts

Various studies give conflicting reports on the relationship between breast cancer and oral contraceptive use. Oral contraceptive use may slightly increase your chance of having breast cancer diagnosed, particularly after using hormonal contraceptives at a younger age. After you stop using hormonal contraceptives, the chances of having breast cancer diagnosed begin to go back down. You should have regular breast examinations by a healthcare professional and examine your own breasts monthly. Tell your healthcare professional if you have a family history of breast cancer or if you have had breast nodules or an abnormal mammogram. Women who currently have or have had breast cancer should not use oral contraceptives because breast cancer is usually a hormone-sensitive tumor.

Some studies have found an increase in the incidence of cancer of the cervix in women who use oral contraceptives. However, this finding may be related to factors other than the use of oral contraceptives. There is insufficient evidence to rule out the possibility that the pill may cause such cancers.

ESTIMATED RISK OF DEATH FROM A BIRTH CONTROL METHOD OR PREGNANCY

All methods of birth control and pregnancy are associated with a risk of developing certain diseases which may lead to disability or death. An estimate of the number of deaths associated with different methods of birth control and pregnancy has been calculated and is shown in the following table.

Annual Number of Birth-Related or Method-Related Deaths associated With Control of Fertility Per 100,000 Non sterile Women, by Fertility Control Method According To Age
Method of control and outcome | 15–19 | 20–24 | 25–29 | 30–34 | 35–39 | 40–44
No fertility control methods [Deaths are birth-related] | 7.0 | 7.4 | 9.1 | 14.8 | 25.7 | 28.2
Oral contraceptives non-smoker [Deaths are method-related] | 0.3 | 0.5 | 0.9 | 1.9 | 13.8 | 31.6
Oral contraceptives smoker | 2.2 | 3.4 | 6.6 | 13.5 | 51.1 | 117.2
IUD | 0.8 | 0.8 | 1.0 | 1.0 | 1.4 | 1.4
Condom | 1.1 | 1.6 | 0.7 | 0.2 | 0.3 | 0.4
Diaphragm/spermicide | 1.9 | 1.2 | 1.2 | 1.3 | 2.2 | 2.8
Periodic abstinence | 2.5 | 1.6 | 1.6 | 1.7 | 2.9 | 3.6
Adapted from H.W. Ory, ref. #35.

In the above table, the risk of death from any birth control method is less than the risk of childbirth, except for oral contraceptive users over the age of 35 who smoke and pill users over the age of 40 even if they do not smoke. It can be seen in the table that for women aged 15 to 39, the risk of death was highest with pregnancy (7 to 26 deaths per 100,000 women, depending on age). Among pill users who do not smoke, the risk of death was always lower than that associated with pregnancy for any age group less than 40. Over the age of 40, the risk increases to 32 deaths per 100,000 women, compared to 28 associated with pregnancy in that age group. However, for pill users who smoke and are over the age of 35, the estimated number of deaths exceeds those for other methods of birth control. If a woman is over the age of 40 and smokes, her estimated risk of death is four times higher (117/100,000 women) than the estimated risk associated with pregnancy (28/100,000 women) in that age group.

The suggestion that women over 40 who do not smoke should not take oral contraceptives is based on information from older, higher-dose pills. An Advisory Committee of the FDA discussed this issue in 1989 and recommended that the benefits of low-dose oral contraceptive use by healthy, non-smoking women over 40 years of age may outweigh the possible risks. Older women, as all women, who take oral contraceptives, should take an oral contraceptive which contains the least amount of estrogen and progestogen that is compatible with the individual patient needs.

WARNING SIGNALS

If any of these adverse effects occur while you are taking oral contraceptives, call your healthcare professional immediately:

- Sharp chest pain, coughing of blood, or sudden shortness of breath (indicating a possible clot in the lung)
- Pain in the calf (indicating a possible clot in the leg)
- Crushing chest pain or heaviness in the chest (indicating a possible heart attack)
- Sudden severe headache or vomiting, dizziness or fainting, disturbances of vision or speech, weakness, or numbness in an arm or leg (indicating a possible stroke)
- Sudden partial or complete loss of vision (indicating a possible clot in the eye)
- Breast lumps (indicating possible breast cancer or fibrocystic disease of the breast; ask your healthcare professional to show you how to examine your breasts)
- Severe pain or tenderness in the stomach area (indicating a possibly ruptured liver tumor)
- Difficulty in sleeping, weakness, lack of energy, fatigue, or change in mood (possibly indicating severe depression)
- Jaundice or a yellowing of the skin or eyeballs, accompanied frequently by fever, fatigue, loss of appetite, dark colored urine, or light colored bowel movements (indicating possible liver problems)

SIDE EFFECTS OF ORAL CONTRACEPTIVES

In addition to the risks and more serious side effects discussed above, the following may also occur:

1. Irregular vaginal bleeding

Irregular vaginal bleeding or spotting may occur while you are taking the pills. Irregular bleeding may vary from slight staining between menstrual periods to breakthrough bleeding which is a flow much like a regular period. Irregular bleeding occurs most often during the first few months of oral contraceptive use, but may also occur after you have been taking the pill for some time. Such bleeding may be temporary and usually does not indicate any serious problems. It is important to continue taking your pills on schedule. If the bleeding occurs in more than one cycle or lasts for more than a few days, talk to your healthcare professional.

2. Contact Lenses

If you wear contact lenses and notice a change in vision or an inability to wear your lenses, contact your healthcare professional.

3. Fluid Retention

Oral contraceptives may cause edema (fluid retention) with swelling of the fingers or ankles and may raise your blood pressure. If you experience fluid retention, contact your healthcare professional.

4. Melasma

A spotty darkening of the skin is possible, particularly of the face, which may persist.

5. Other Side Effects

Other side effects may include nausea and vomiting, change in appetite, headache, nervousness, depression, dizziness, loss of scalp hair, rash, vaginal infections, and allergic reactions.

If any of these side effects bother you, call your healthcare professional.

GENERAL PRECAUTIONS

1. Missed Periods and Use of Oral Contraceptives Before or During Early Pregnancy

There may be times when you may not menstruate regularly after you have completed taking a cycle of pills. If you have taken your pills regularly and miss one menstrual period, continue taking your pills for the next cycle but be sure to inform your healthcare professional. If you have not taken the pills daily as instructed and missed a menstrual period, or if you missed two consecutive menstrual periods, you may be pregnant. . Check with your healthcare professional immediately to determine whether you are pregnant. Stop taking your pills if you are pregnant.

There is no conclusive evidence that oral contraceptive use is associated with an increase in birth defects, when taken inadvertently during early pregnancy. Previously, a few studies had reported that oral contraceptives might be associated with birth defects, but these findings have not been seen in more recent studies. Nevertheless, oral contraceptives should not be used during pregnancy. You should check with your healthcare professional about risks to your unborn child of any medication taken during pregnancy.

2. While Breast Feeding

If you are breast feeding, consult your healthcare professional before starting oral contraceptives. Some of the drug will be passed on to the child in the milk. A few adverse effects on the child have been reported, including yellowing of the skin (jaundice) and breast enlargement. In addition, combination oral contraceptives may decrease the amount and quality of your milk. If possible, do not use combination oral contraceptives while breast feeding. You should use another method of contraception since breast feeding provides only partial protection from becoming pregnant and this partial protection decreases significantly as you breast feed for longer periods of time. You should consider starting combination oral contraceptives only after you have weaned your child completely.

3. Laboratory Tests

If you are scheduled for any laboratory tests, tell your healthcare professional you are taking birth control pills. Certain blood tests may be affected by birth control pills.

4. Drug Interactions

Certain drugs may interact with birth control pills to make them less effective in preventing pregnancy or cause an increase in breakthrough bleeding. Such drugs include rifampin, drugs used for epilepsy such as barbiturates (for example, phenobarbital), topiramate (Topamax®), carbamazepine (Tegretol® is one brand of this drug), or phenytoin (Dilantin® is one brand of this drug), phenylbutazone (Butazolidin® is one brand), certain drugs used in the treatment of HIV or AIDS, and possibly certain antibiotics. Medicine for pulmonary hypertension, such as bosentan (Tracleer®). Pregnancies and breakthrough bleeding have been reported by women who also used some form of the herbal supplement St. John's Wort while using combined hormonal contraceptives. Hormonal contraceptives may interact with lamotrigine (LAMICTAL®), an anticonvulsant used for epilepsy. This may increase the risk of seizures so your healthcare professional may need to adjust the dose of lamotrigine. You may need to use additional contraception when you take drugs which can make oral contraceptives less effective. Be sure to tell your healthcare professional if you are taking or start taking any medications while taking birth control pills.

5. Sexually Transmitted Diseases

ORTHO-CYCLEN® and ORTHO TRI-CYCLEN® (like all oral contraceptives) are intended to prevent pregnancy. Oral contraceptives do not protect against transmission of HIV (AIDS) and other sexually transmitted diseases such as chlamydia, genital herpes, genital warts, gonorrhea, hepatitis B, and syphilis.

HOW TO TAKE THE PILL

IMPORTANT POINTS TO REMEMBER

BEFORE YOU START TAKING YOUR PILLS:

1. BE SURE TO READ THESE DIRECTIONS:
  Before you start taking your pills.
  Anytime you are not sure what to do.
2. THE RIGHT WAY TO TAKE THE PILL IS TO TAKE ONE PILL EVERY DAY AT THE SAME TIME.
  If you miss pills you could get pregnant. This includes starting the pack late.
  The more pills you miss, the more likely you are to get pregnant.
3. MANY WOMEN HAVE SPOTTING OR LIGHT BLEEDING, OR MAY FEEL SICK TO THEIR STOMACH DURING THE FIRST 1–3 PACKS OF PILLS. If you feel sick to your stomach or have spotting or light bleeding, do not stop taking the pill. The problem will usually go away. If it doesn't go away, check with your healthcare professional.
4. MISSING PILLS CAN ALSO CAUSE SPOTTING OR LIGHT BLEEDING, even when you make up these missed pills.
  On the days you take 2 pills to make up for missed pills, you could also feel a little sick to your stomach.
5. IF YOU HAVE VOMITING OR DIARRHEA, OR IF YOU TAKE SOME MEDICINES, including some antibiotics, your pills may not work as well.
  Use a back-up method (such as condoms or spermicide) until you check with your healthcare professional.
6. IF YOU HAVE TROUBLE REMEMBERING TO TAKE THE PILL, talk to your healthcare professional about how to make pill-taking easier or about using another method of birth control.
7. IF YOU HAVE ANY QUESTIONS OR ARE UNSURE ABOUT THE INFORMATION IN THIS LEAFLET, call your healthcare professional.

BEFORE YOU START TAKING YOUR PILLS

1. DECIDE WHAT TIME OF DAY YOU WANT TO TAKE YOUR PILL.
  It is important to take it at about the same time every day.
2. LOOK AT YOUR PILL PACK
  The pill pack has 21 "active" pills (with hormones) to take for 3 weeks. This is followed by 1 week of "reminder" dark green pills (without hormones).
  ORTHO TRI-CYCLEN®: There are 7 white "active" pills, 7 light blue "active" pills, 7 blue "active" pills, and 7 dark green "reminder" pills.
  ORTHO-CYCLEN®: There are 21 blue "active" pills and 7 dark green "reminder" pills.
3. ALSO FIND:
  1) where on the pack to start taking pills,
  2) in what order to take the pills.

CHECK PICTURE OF PILL PACK AND ADDITIONAL INSTRUCTIONS FOR USING THIS PACKAGE IN THE BRIEF SUMMARY PATIENT PACKAGE INSERT.

4. BE SURE YOU HAVE READY AT ALL TIMES:
  ANOTHER KIND OF BIRTH CONTROL (such as condoms or spermicide) to use as a back-up method in case you miss pills.
  AN EXTRA, FULL PILL PACK.

WHEN TO START THE FIRST PACK OF PILLS

You have a choice of which day to start taking your first pack of pills. ORTHO TRI-CYCLEN® and ORTHO-CYCLEN® are available in the DIALPAK® Tablet Dispenser which is preset for a Sunday Start. Day 1 Start is also provided. Decide with your healthcare professional which is the best day for you. Pick a time of day which will be easy to remember.

Sunday Start:

ORTHO TRI-CYCLEN®: Take the first white "active" pill of the first pack on the Sunday after your period starts, even if you are still bleeding. If your period begins on Sunday, start the pack that same day.

ORTHO-CYCLEN®: Take the first blue "active" pill of the first pack on the Sunday after your period starts, even if you are still bleeding. If your period begins on Sunday, start the pack that same day.

Use another method of birth control such as condoms or spermicide as a back-up method if you have sex anytime from the Sunday you start your first pack until the next Sunday (7 days).

Day 1 Start:

ORTHO TRI-CYCLEN®: Take the first white "active" pill of the first pack during the first 24 hours of your period.

ORTHO-CYCLEN®: Take the first blue "active" pill of the first pack during the first 24 hours of your period.

You will not need to use a back-up method of birth control, since you are starting the pill at the beginning of your period.

WHAT TO DO DURING THE MONTH

1. Take One Pill at the Same Time Every Day Until the Pack is Empty.
  Do not skip pills even if you are spotting or bleeding between monthly periods or feel sick to your stomach (nausea).
  Do not skip pills even if you do not have sex very often.
2. When You Finish a Pack or Switch Your Brand of Pills:
  Start the next pack on the day after your last "reminder" pill. Do not wait any days between packs.

WHAT TO DO IF YOU MISS PILLS

ORTHO TRI-CYCLEN®:

If you MISS 1 white, light blue or blue "active" pill:

1. Take it as soon as you remember. Take the next pill at your regular time. This means you may take 2 pills in 1 day.
2. You do not need to use a back-up birth control method if you have sex.

If you MISS 2 white or light blue "active" pills in a row in WEEK 1 OR WEEK 2 of your pack:

1. Take 2 pills on the day you remember and 2 pills the next day.
2. Then take 1 pill a day until you finish the pack.
3. You COULD BECOME PREGNANT if you have sex in the 7 days after you miss pills. You MUST use another birth control method (such as condoms or spermicide) as a back-up method for those 7 days.

If you MISS 2 blue "active" pills in a row in THE 3RD WEEK:

1. If you are a Sunday Starter:
  Keep taking 1 pill every day until Sunday. On Sunday, THROW OUT the rest of the pack and start a new pack of pills that same day.
  If you are a Day 1 Starter:
  THROW OUT the rest of the pill pack and start a new pack that same day.
2. You may not have your period this month but this is expected. However, if you miss your period 2 months in a row, call your healthcare professional because you might be pregnant.
3. You COULD BECOME PREGNANT if you have sex in the 7 days after you miss pills. You MUST use another birth control method (such as condoms or spermicide) as a back-up method for those 7 days.

If you MISS 3 OR MORE white, light blue or blue "active" pills in a row (during the first 3 weeks):

1. If you are a Sunday Starter:
  Keep taking 1 pill every day until Sunday. On Sunday, THROW OUT the rest of the pack and start a new pack of pills that same day.
  If you are a Day 1 Starter:
  THROW OUT the rest of the pill pack and start a new pack that same day.
2. You may not have your period this month but this is expected. However, if you miss your period 2 months in a row, call your healthcare professional because you might be pregnant.
3. You COULD BECOME PREGNANT if you have sex in the 7 days after you miss pills. You MUST use another birth control method (such as condoms or spermicide) as a back-up method for those 7 days.

ORTHO-CYCLEN®:

If you MISS 1 blue "active" pill:

1. Take it as soon as you remember. Take the next pill at your regular time. This means you may take 2 pills in 1 day.
2. You do not need to use a back-up birth control method if you have sex.

If you MISS 2 blue "active" pills in a row in WEEK 1 OR WEEK 2 of your pack:

1. Take 2 pills on the day you remember and 2 pills the next day.
2. Then take 1 pill a day until you finish the pack.
3. You COULD BECOME PREGNANT if you have sex in the 7 days after you miss pills. You MUST use another birth control method (such as condoms or spermicide) as a back-up method for those 7 days.

If you MISS 2 blue "active" pills in a row in THE 3RD WEEK:

1. If you are a Sunday Starter:
  Keep taking 1 pill every day until Sunday. On Sunday, THROW OUT the rest of the pack and start a new pack of pills that same day.
  If you are a Day 1 Starter:
  THROW OUT the rest of the pill pack and start a new pack that same day.
2. You may not have your period this month but this is expected. However, if you miss your period 2 months in a row, call your healthcare professional because you might be pregnant.
3. You COULD BECOME PREGNANT if you have sex in the 7 days after you miss pills. You MUST use another birth control method (such as condoms or spermicide) as a back-up method for those 7 days.

If you MISS 3 OR MORE blue "active" pills in a row (during the first 3 weeks):

1. If you are a Sunday Starter:
  Keep taking 1 pill every day until Sunday. On Sunday, THROW OUT the rest of the pack and start a new pack of pills that same day.
  If you are a Day 1 Starter:
  THROW OUT the rest of the pill pack and start a new pack that same day.
2. You may not have your period this month but this is expected. However, if you miss your period 2 months in a row, call your healthcare professional because you might be pregnant.
3. You COULD BECOME PREGNANT if you have sex in the 7 days after you miss pills. You MUST use another birth control method (such as condoms or spermicide) as a back-up method for those 7 days.

A REMINDER:

If you forget any of the 7 dark green "reminder" pills in Week 4:

THROW AWAY the pills you missed.

Keep taking 1 pill each day until the pack is empty.

You do not need a back-up method.

FINALLY, IF YOU ARE STILL NOT SURE WHAT TO DO ABOUT THE PILLS YOU HAVE MISSED:

Use a BACK-UP METHOD anytime you have sex.

KEEP TAKING ONE "ACTIVE" PILL EACH DAY until you can reach your healthcare professional.

PREGNANCY DUE TO PILL FAILURE

The incidence of pill failure resulting in pregnancy is approximately 5%, including women who do not always take the pills exactly as directed. If failure does occur, the risk to the fetus is minimal.

PREGNANCY AFTER STOPPING THE PILL

There may be some delay in becoming pregnant after you stop using oral contraceptives, especially if you had irregular menstrual cycles before you used oral contraceptives. It may be advisable to postpone conception until you begin menstruating regularly once you have stopped taking the pill and desire pregnancy.

There does not appear to be any increase in birth defects in newborn babies when pregnancy occurs soon after stopping the pill.

OVERDOSAGE

Serious ill effects have not been reported following ingestion of large doses of oral contraceptives by young children. Overdosage may cause nausea and withdrawal bleeding in females. In case of overdosage, contact your healthcare professional or pharmacist.

OTHER INFORMATION

Your healthcare professional will take a medical and family history before prescribing oral contraceptives and will examine you. The physical examination may be delayed to another time if you request it and the healthcare professional believes that it is a good medical practice to postpone it. You should be reexamined at least once a year. Be sure to inform your healthcare professional if there is a family history of any of the conditions listed previously in this leaflet. Be sure to keep all appointments with your healthcare professional, because this is a time to determine if there are early signs of side effects of oral contraceptive use.

Do not use the drug for any condition other than the one for which it was prescribed. This drug has been prescribed specifically for you; do not give it to others who may want birth control pills.

HEALTH BENEFITS FROM ORAL CONTRACEPTIVES

In addition to preventing pregnancy, use of combination oral contraceptives may provide certain benefits. They are:

- menstrual cycles may become more regular
- blood flow during menstruation may be lighter and less iron may be lost. Therefore, anemia due to iron deficiency is less likely to occur
- pain or other symptoms during menstruation may be encountered less frequently
- ectopic (tubal) pregnancy may occur less frequently
- noncancerous cysts or lumps in the breast may occur less frequently
- acute pelvic inflammatory disease may occur less frequently
- oral contraceptive use may provide some protection against developing two forms of cancer: cancer of the ovaries and cancer of the lining of the uterus.

If you want more information about birth control pills, ask your healthcare professional or pharmacist. They have a more technical leaflet called the Professional Labeling, which you may wish to read. The professional labeling is also published in a book entitled Physicians' Desk Reference, available in many book stores and public libraries.

Keep out of reach of children.

Store at 25°C (77°F); excursions permitted to 15–30°C (59–86°F).

Protect from light.

(LOGO)

Mfd. for:

Ortho Women's Health & Urology, Division of Ortho-McNeil-Janssen Pharmaceuticals, Inc.
Raritan, New Jersey 08869

Mfd. by:

Janssen Ortho, LLC
Manati, Puerto Rico 00674

© Ortho-McNeil-Janssen Pharmaceuticals, Inc. 1998 Revised August 2008 635-50-900-

Printed in U.S.A.

Relabeling "Additional barcode label" by:
Physicians Total Care, Inc.
Tulsa, OK 74146

PACKAGE LABEL

PRINCIPAL DISPLAY PANEL - Ortho Tri-Cyclen Pouch

28 Day Regimen

NDC 54868-4093-0

REFILL

ORTHO
TRI~CYCLEN®
(norgestimate/ethinyl estradiol)

NOW!
SMALLER
PILLS

Each white tablet contains 0.180 mg norgestimate and 0.035 mg
ethinyl estradiol. Each light blue tablet contains 0.215 mg
norgestimate and 0.035 mg ethinyl estradiol. Each blue tablet
contains 0.250 mg norgestimate and 0.035 mg ethinyl estradiol.
Each green tablet contains inert ingredients.

This product (like all oral contraceptives) is intended to
prevent pregnancy. It does not protect against HIV
infection (AIDS) and other sexually transmitted diseases.

Rx only.

Dosage: One tablet daily as prescribed. See package insert.
Store at 25°C (77°F); excursions permitted to 15°-30°C (59°-86°F).
Keep out of reach of children. Protect from light.